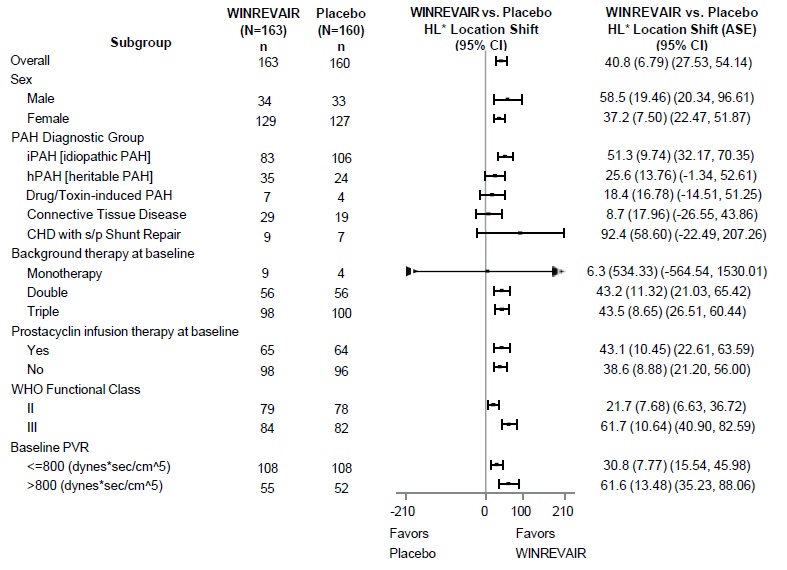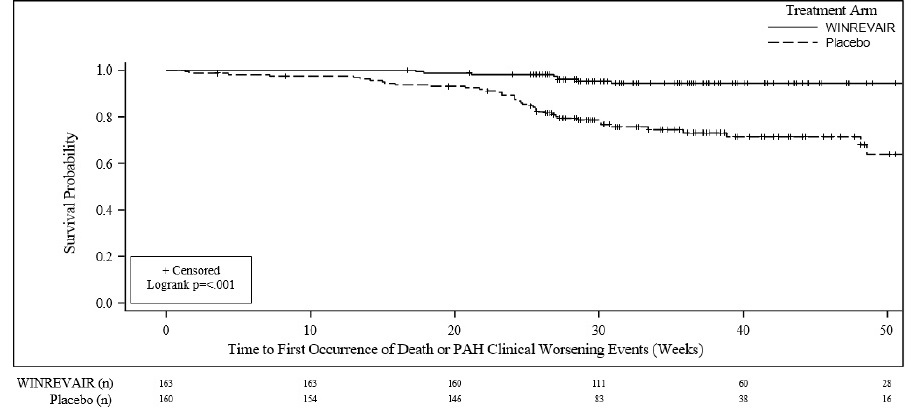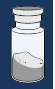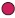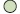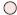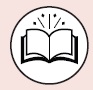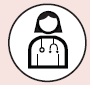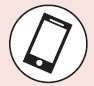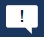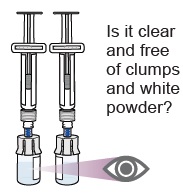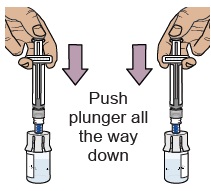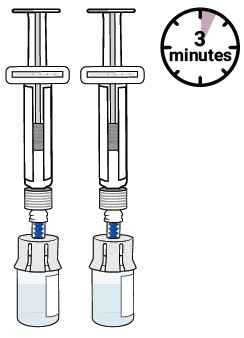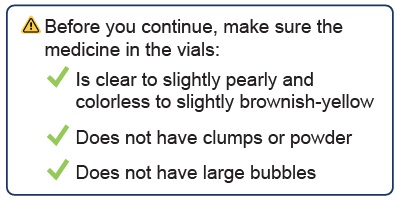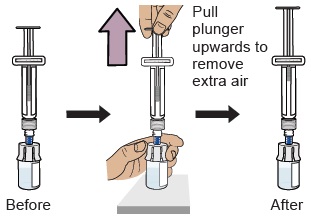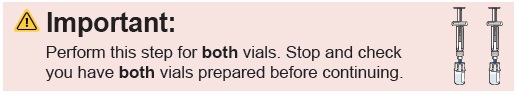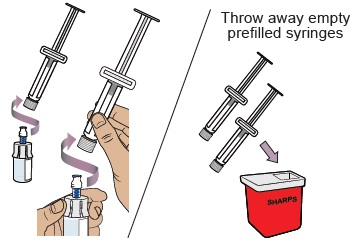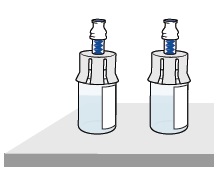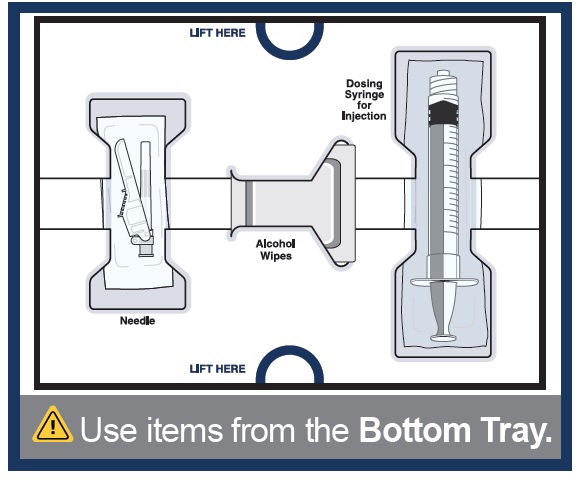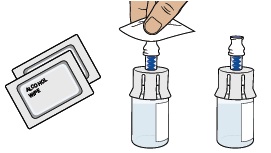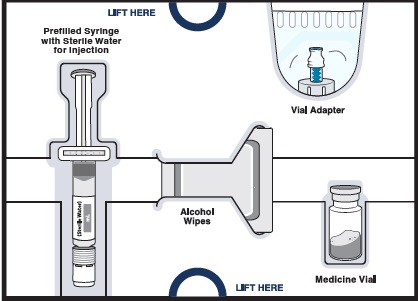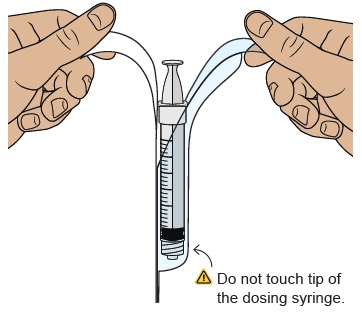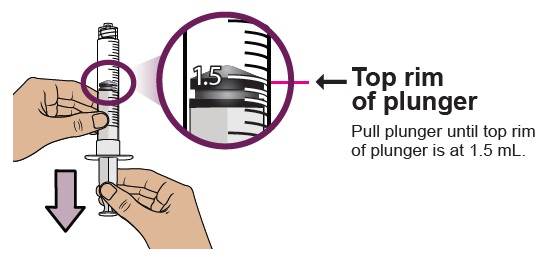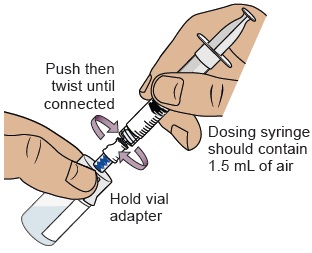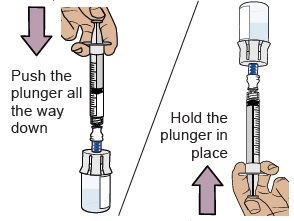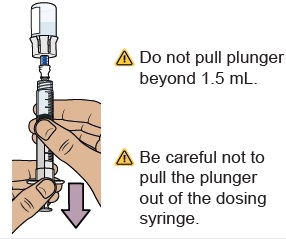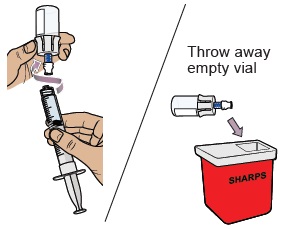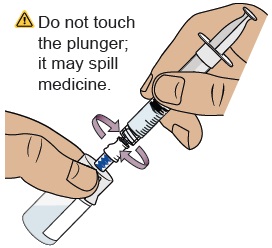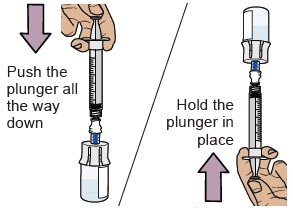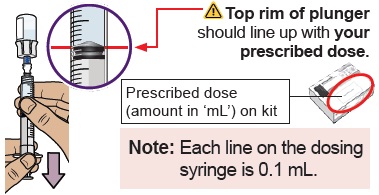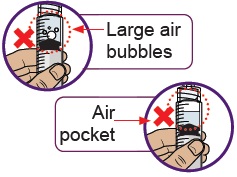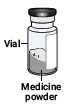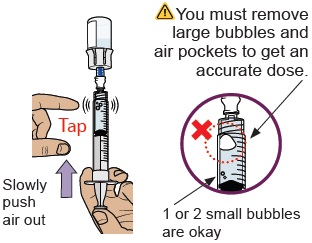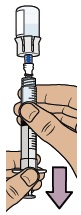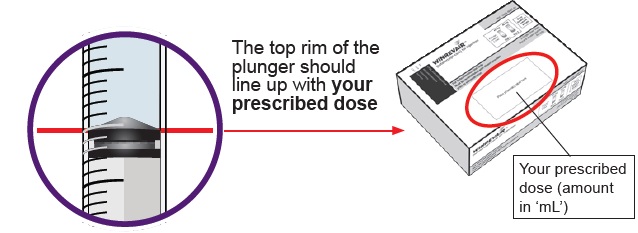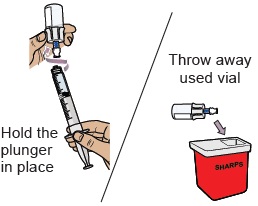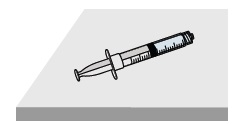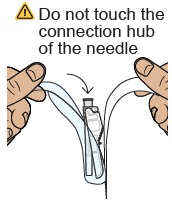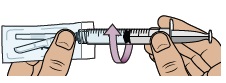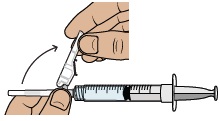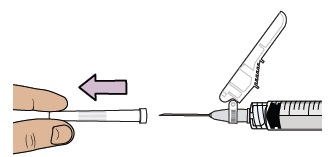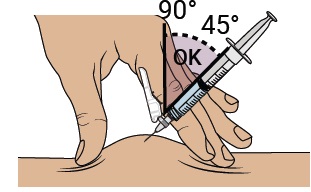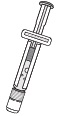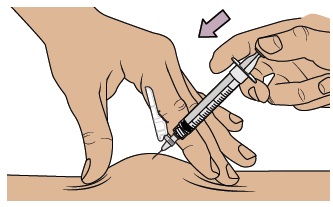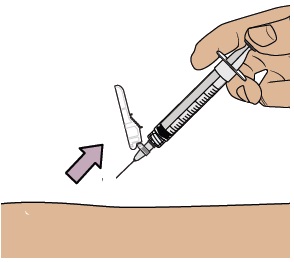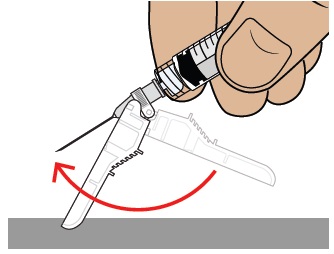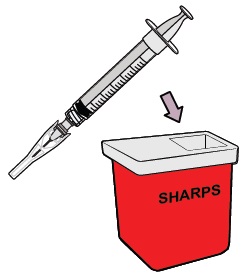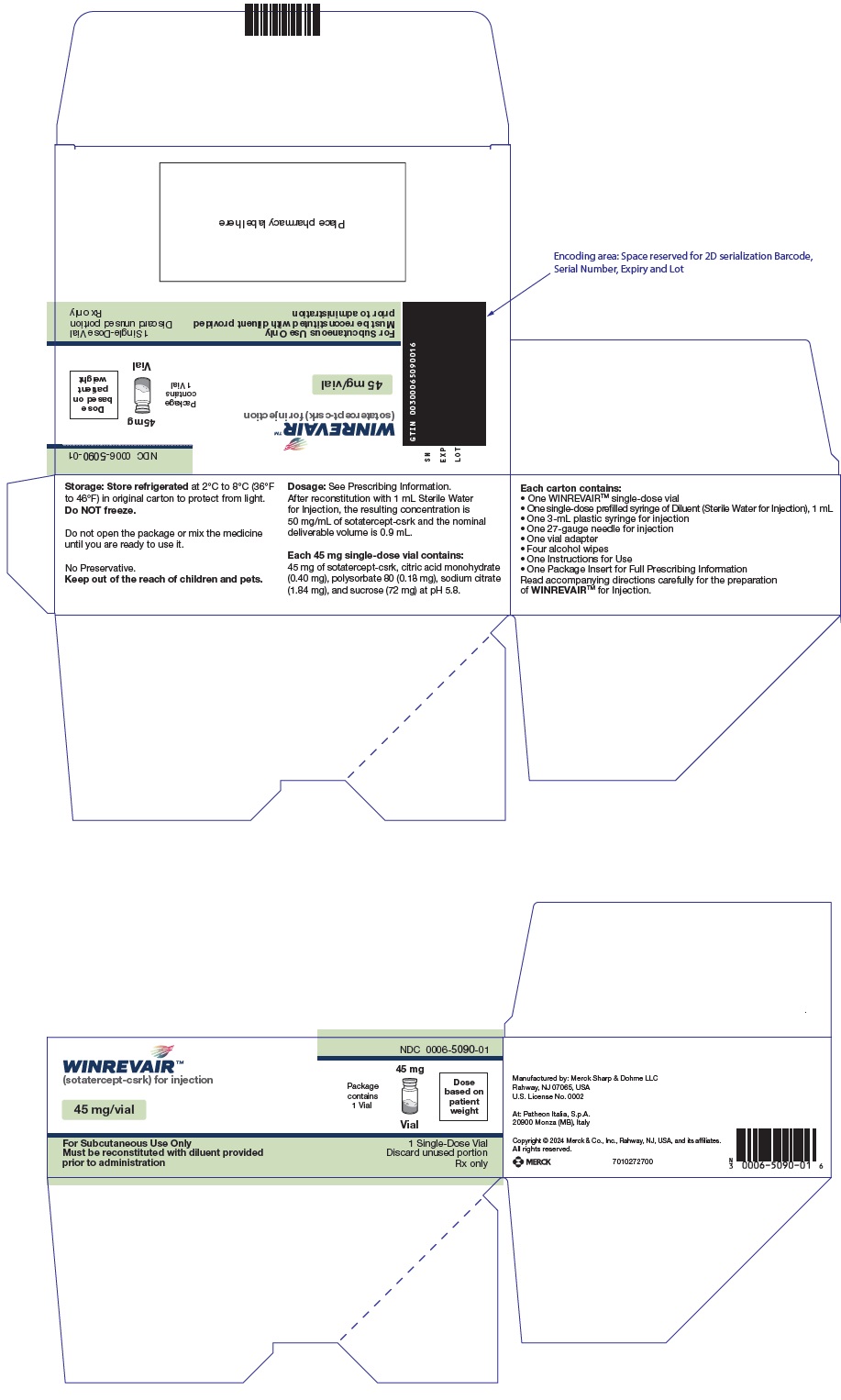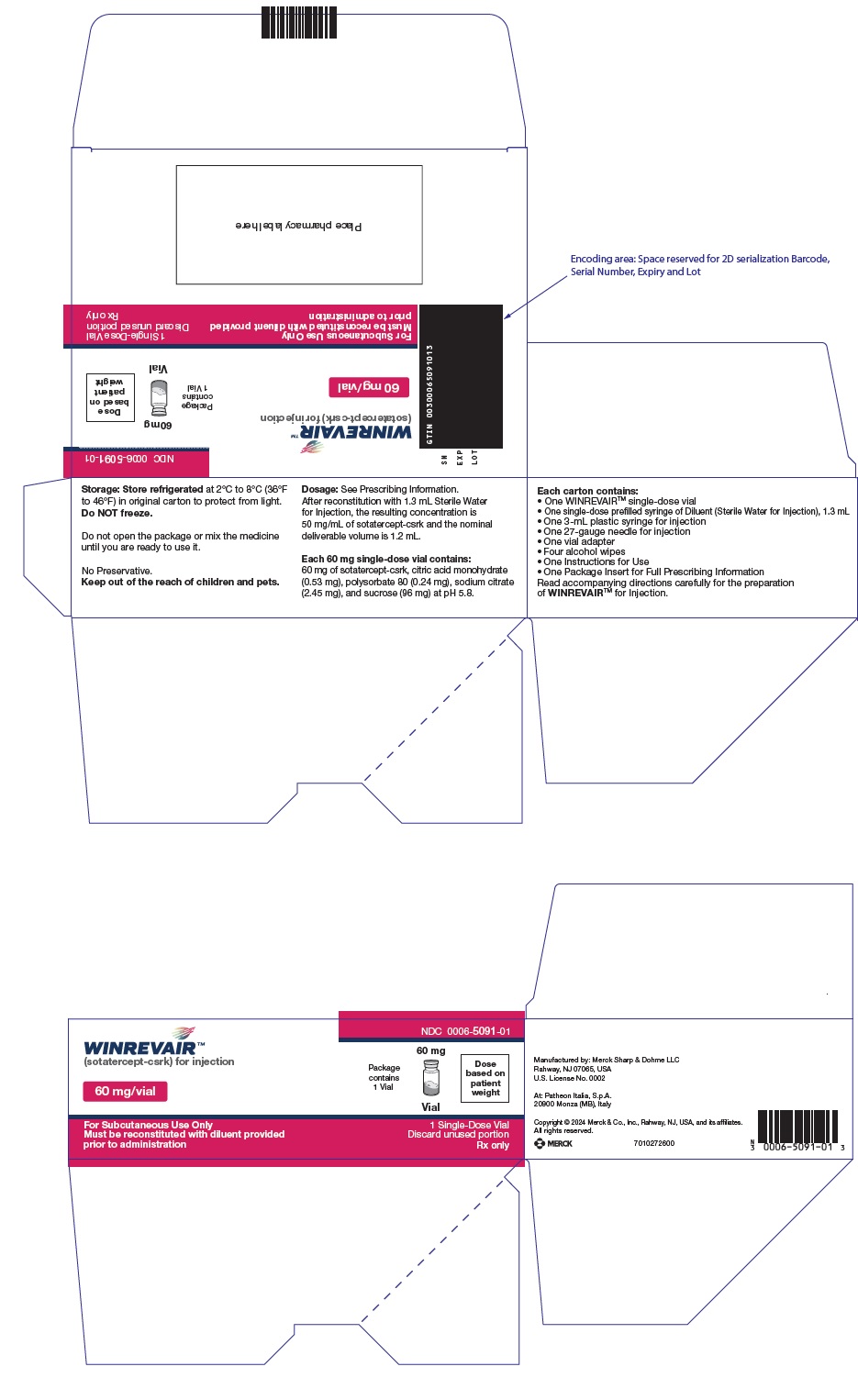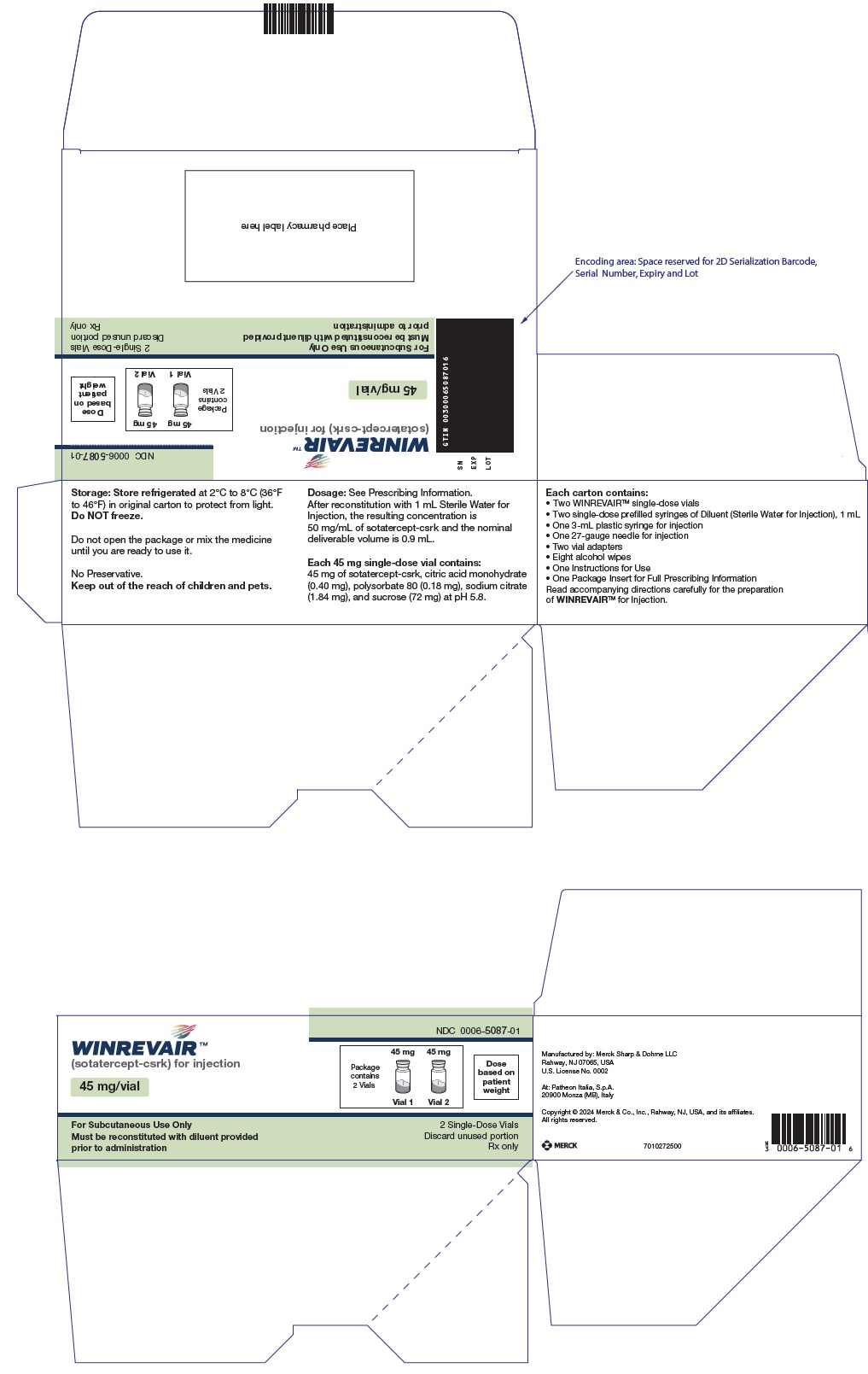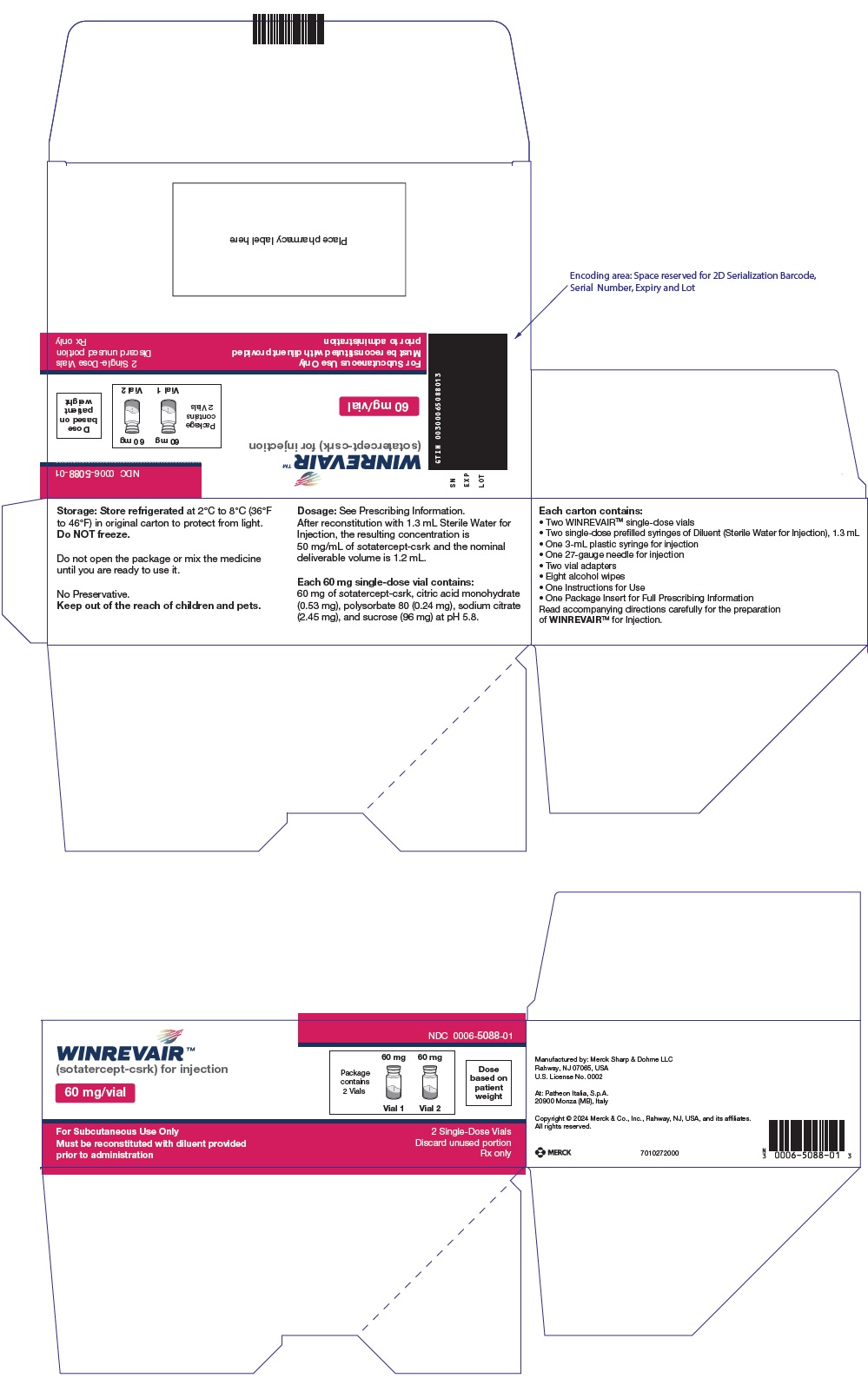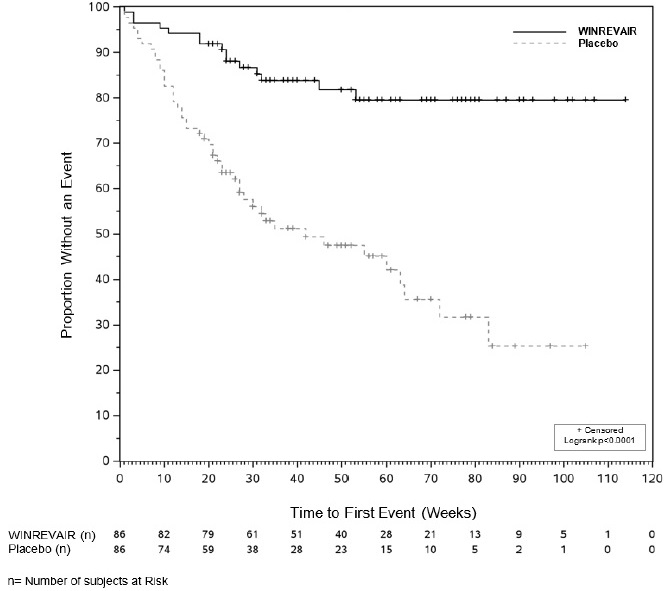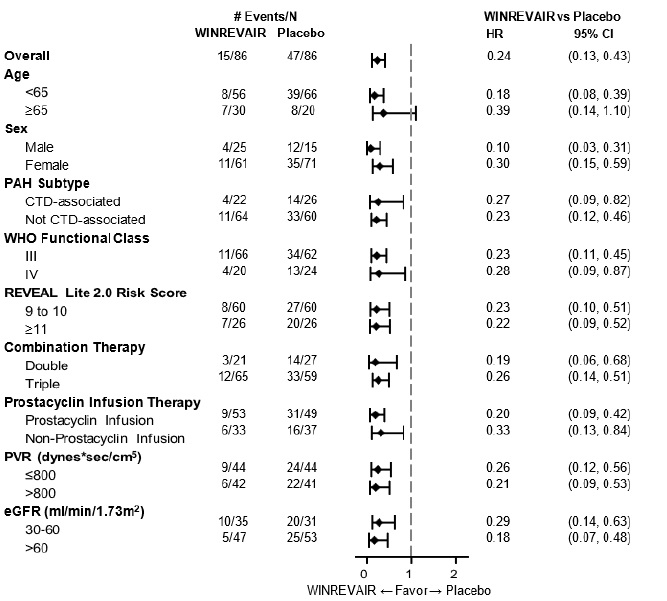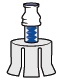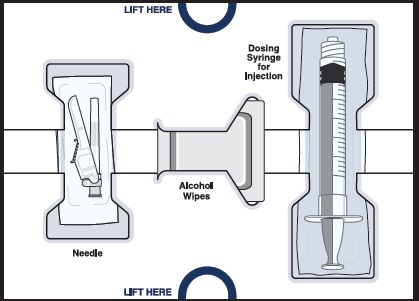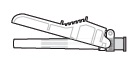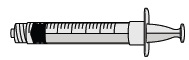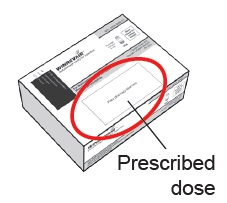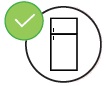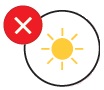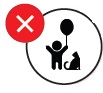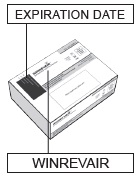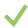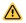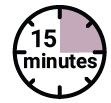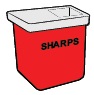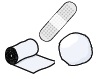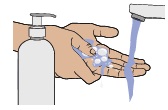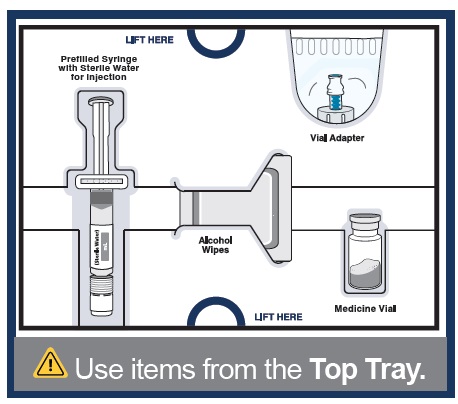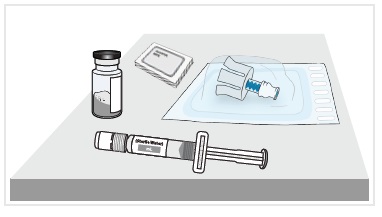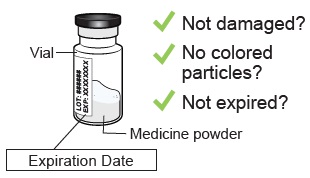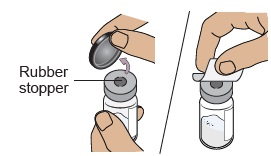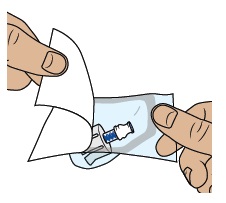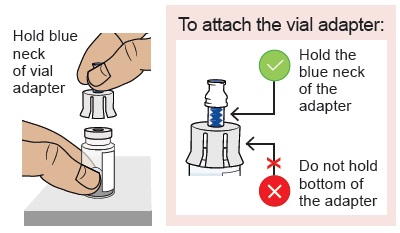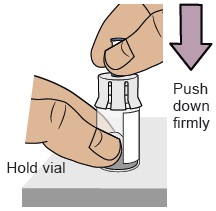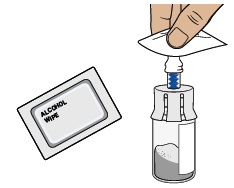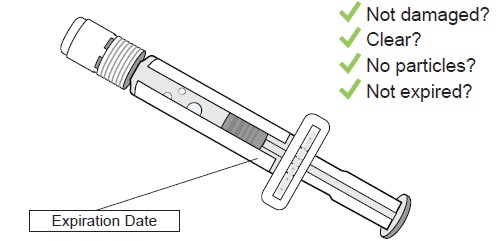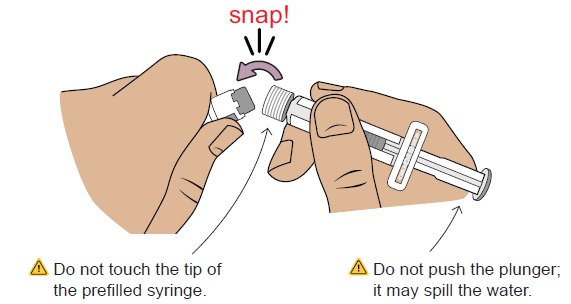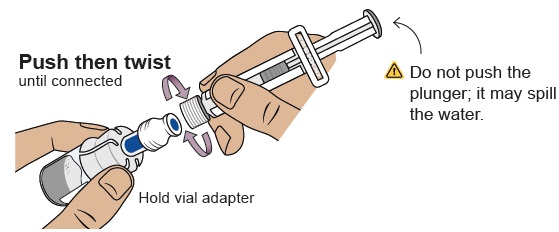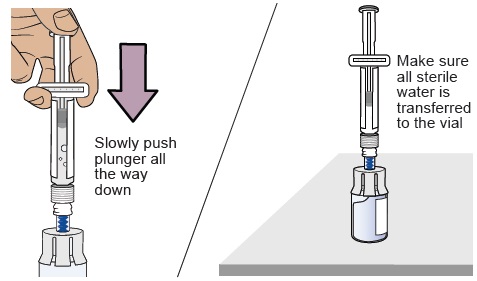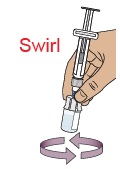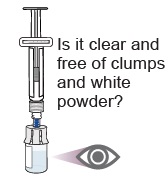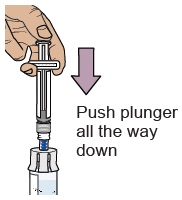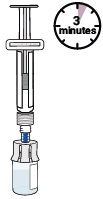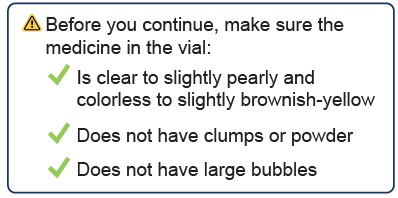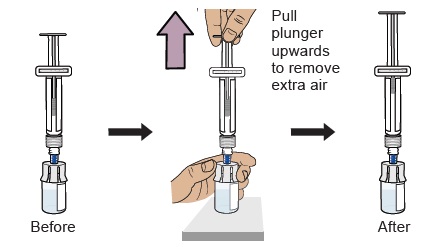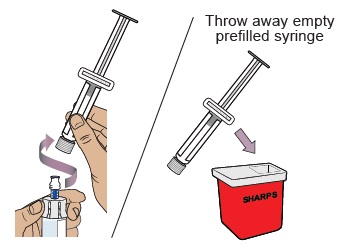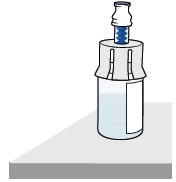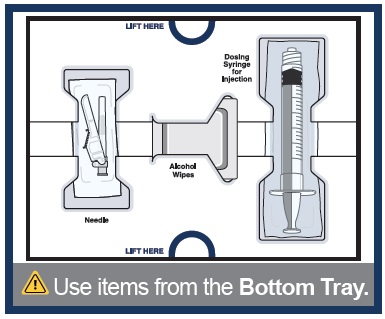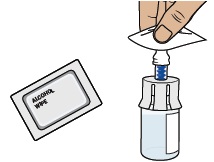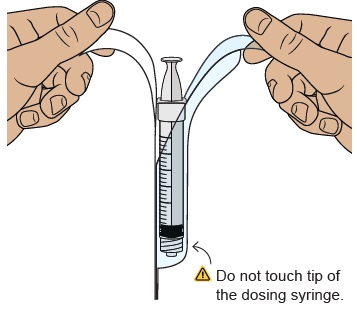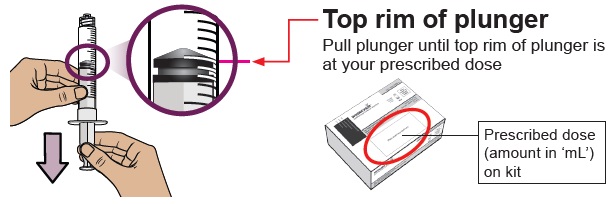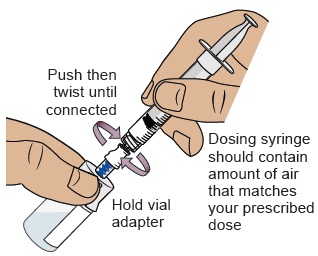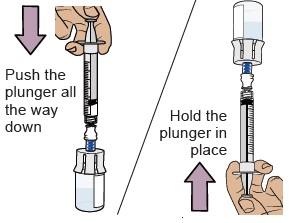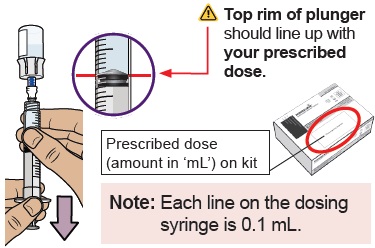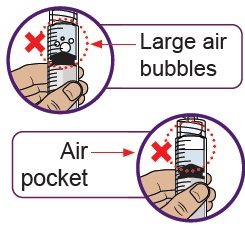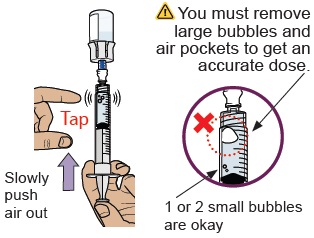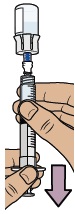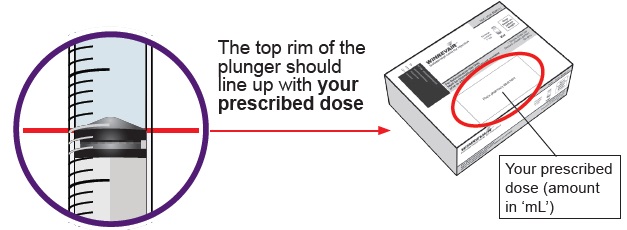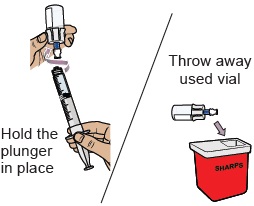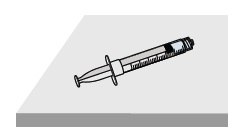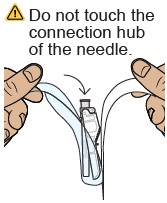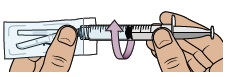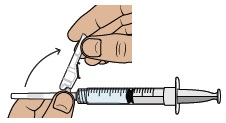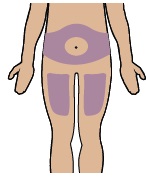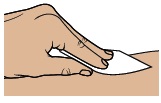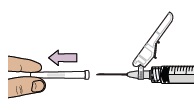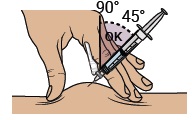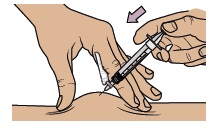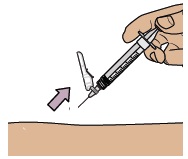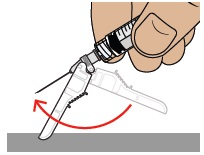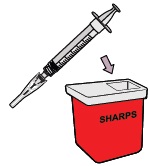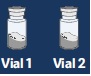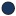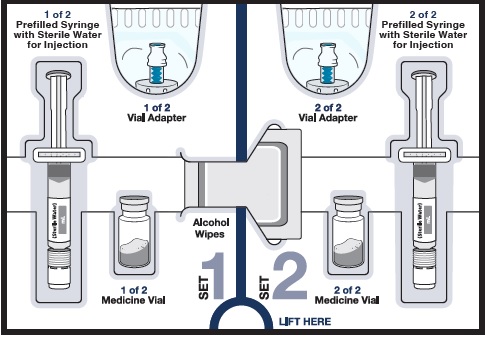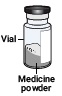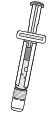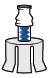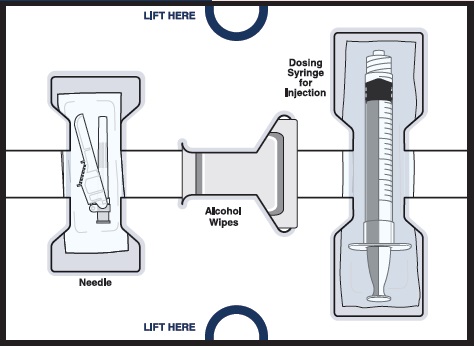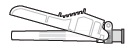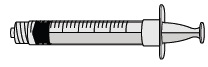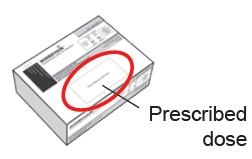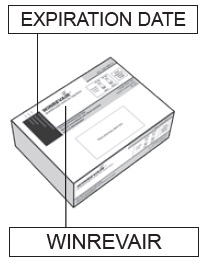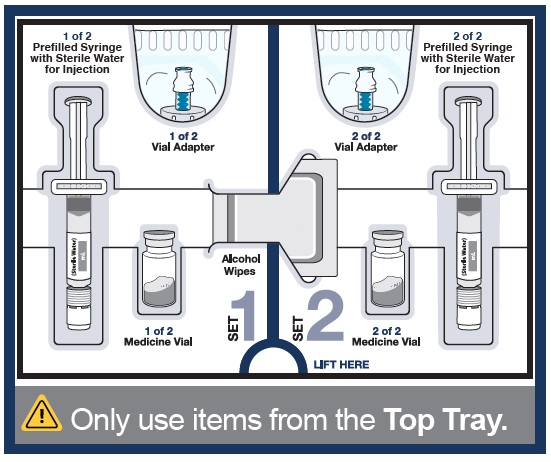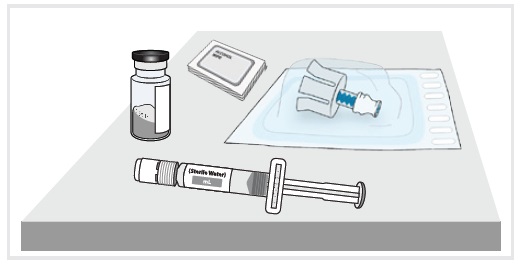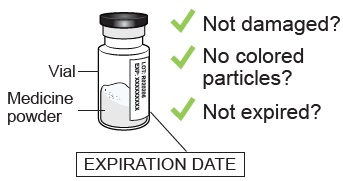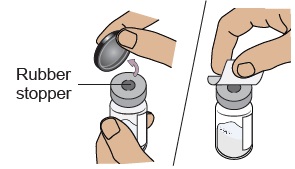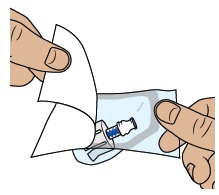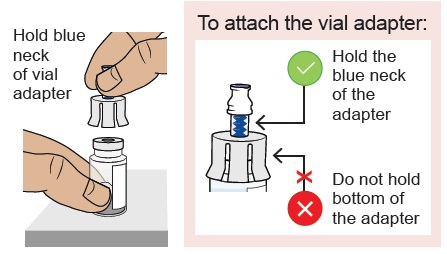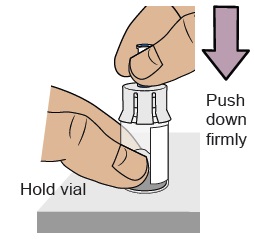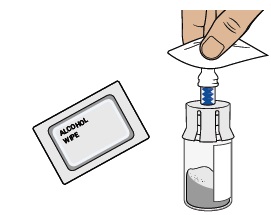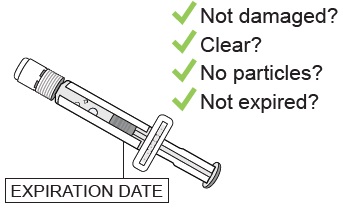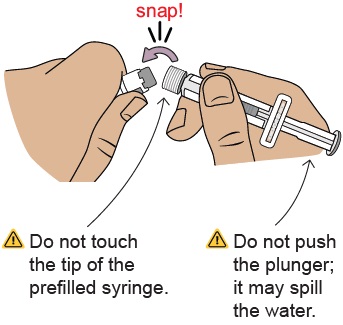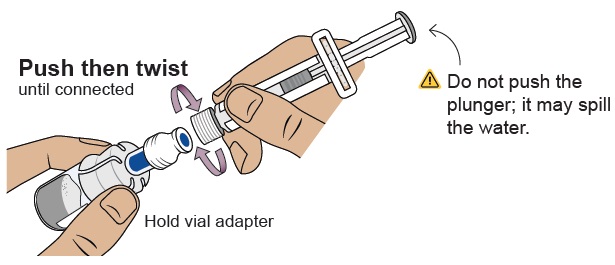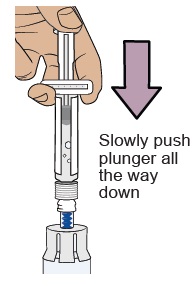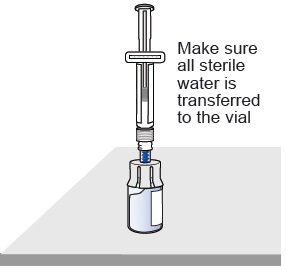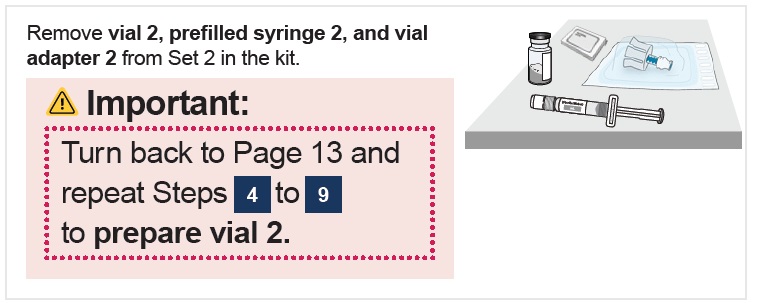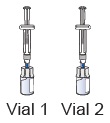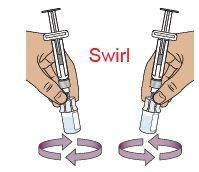 DRUG LABEL: WINREVAIR
NDC: 0006-5090 | Form: KIT | Route: SUBCUTANEOUS
Manufacturer: Merck Sharp & Dohme LLC
Category: prescription | Type: HUMAN PRESCRIPTION DRUG LABEL
Date: 20251208

ACTIVE INGREDIENTS: SOTATERCEPT 45 mg/1 mL; WATER 1 mL/1 mL
INACTIVE INGREDIENTS: CITRIC ACID MONOHYDRATE 0.40 mg/1 mL; POLYSORBATE 80 0.18 mg/1 mL; SUCROSE 72 mg/1 mL; TRISODIUM CITRATE DIHYDRATE 2.1 mg/1 mL

HIGHLIGHTS OF PRESCRIBING INFORMATION

These highlights do not include all the information needed to use WINREVAIR safely and effectively. See full prescribing information for WINREVAIR.
WINREVAIR™ (sotatercept-csrk) for injection, for subcutaneous use
Initial U.S. Approval: 2024

RECENT MAJOR CHANGES

Indications and Usage (1) | 10/2025

1 INDICATIONS AND USAGE

WINREVAIR is an activin signaling inhibitor indicated for the treatment of adults with pulmonary arterial hypertension (PAH, WHO Group 1 pulmonary hypertension) to improve exercise capacity and WHO functional class (FC), and reduce the risk of clinical worsening events, including hospitalization for PAH, lung transplantation and death. (1)

2 DOSAGE AND ADMINISTRATION

- The recommended starting dose is 0.3 mg/kg by subcutaneous injection. (2.1)
- The recommended target dose is 0.7 mg/kg every 3 weeks by subcutaneous injection. (2.2)
- Dosage modifications due to increased hemoglobin (Hgb) and decreased platelets may be necessary. Check Hgb and platelets before each dose for the first 5 doses, or longer if values are unstable, and monitor periodically thereafter. (2.3)
- See full prescribing information for preparation and administration instructions. (2.4)

3 DOSAGE FORMS AND STRENGTHS

- For injection: 45 mg lyophilized cake or powder in a single-dose vial (3)
- For injection: 60 mg lyophilized cake or powder in a single-dose vial (3)

4 CONTRAINDICATIONS

None (4)

5 WARNINGS AND PRECAUTIONS

- Erythrocytosis: If severe, may increase the risk of thromboembolic events and hyperviscosity syndrome. Monitor Hgb before each dose for the first 5 doses, or longer if values are unstable, and periodically thereafter to determine if dose adjustments are required. (5.1)
- Severe Thrombocytopenia: May increase the risk of bleeding. Monitor platelets before each dose for the first 5 doses, or longer if values are unstable, and periodically thereafter to determine if dose adjustments are required. (5.2)
- Serious Bleeding: Serious bleeding events were reported and were more likely with concomitant prostacyclin and/or antithrombotic agents, or with low platelet counts. Do not administer WINREVAIR if the patient is experiencing serious bleeding. (5.3)
- Embryo-Fetal Toxicity: May cause fetal harm. Advise females of reproductive potential of the potential risk to a fetus and use of effective contraception. (5.4, 8.1, 8.3)
- Impaired Fertility: May impair female and male fertility. (5.5, 8.3, 13.1)

6 ADVERSE REACTIONS

The most common (≥10% in patients receiving WINREVAIR and 5% more than placebo) adverse reactions were infections, epistaxis, telangiectasia, diarrhea, headache, rash, increased hemoglobin, dizziness, erythema, and gingival bleeding. (6.1)

To report SUSPECTED ADVERSE REACTIONS, contact Merck Sharp & Dohme LLC at 1-877-888-4231 or FDA at 1-800-FDA-1088 or www.fda.gov/medwatch

8 USE IN SPECIFIC POPULATIONS

Lactation: Breastfeeding not recommended. (8.2)

FULL PRESCRIBING INFORMATION

1 INDICATIONS AND USAGE

WINREVAIR™ is indicated for the treatment of adults with pulmonary arterial hypertension (PAH, Group 1 pulmonary hypertension) to improve exercise capacity and World Health Organization (WHO) functional class (FC), and reduce the risk of clinical worsening events including hospitalization for PAH, lung transplantation and death [see Clinical Studies (14.1)].

2 DOSAGE AND ADMINISTRATION

2.1 Recommended Starting Dosage

WINREVAIR is administered once every 3 weeks by subcutaneous injection according to patient body weight. The starting dose of WINREVAIR is 0.3 mg/kg.

Obtain hemoglobin (Hgb) and platelet count prior to the first dose of WINREVAIR. Do not initiate treatment if platelet count is <50,000/mm^3 (<50 x 10^9/L) [see Dosage and Administration (2.3)].

Injection volume for starting dose is calculated based on patient weight as follows:

Injection Volume (mL) = | Weight (kg) x 0.3 mg/kg
Injection Volume (mL) = | 50 mg/mL

Injection volume should be rounded to the nearest 0.1 mL.

For example: (70 kg x 0.3 mg/kg) ÷ 50 mg/mL = 0.42 mL, rounds to 0.4 mL

See Table 1 for selecting the appropriate kit based on calculated injection volume for starting dose.

Table 1: Kit Type Based on Injection Volume for Dose of 0.3 mg/kg
Injection Volume (mL) | Kit Type
0.2 to 0.9 | 45 mg kit (containing 1 x 45 mg vial)
1 to 1.1 | 60 mg kit (containing 1 x 60 mg vial)

2.2 Recommended Target Dosage

After verifying acceptable Hgb and platelet count, increase to the target dose of 0.7 mg/kg. Continue treatment at 0.7 mg/kg every 3 weeks unless dosage adjustments are required [see Dosage and Administration (2.3)].

Injection volume for target dose is calculated based on patient weight as follows:

Injection Volume (mL) = | Weight (kg) x 0.7 mg/kg
Injection Volume (mL) = | 50 mg/mL

Injection volume should be rounded to the nearest 0.1 mL.

For example: (70 kg x 0.7 mg/kg) ÷ 50 mg/mL = 0.98 mL, rounds to 1 mL

See Table 2 for selecting the appropriate kit based on calculated injection volume for target dose.

Table 2: Kit Type Based on Injection Volume for Dose of 0.7 mg/kg
Injection Volume (mL) | Kit Type
0.4 to 0.9 | 45 mg kit (containing 1 x 45 mg vial)
1 to 1.2 | 60 mg kit (containing 1 x 60 mg vial)
1.3 to 1.8 | 90 mg kit (containing 2 x 45 mg vials)
1.9 to 2.4 | 120 mg kit (containing 2 x 60 mg vials)

Missed Dose, Overdose, and Underdose

If a dose of WINREVAIR is missed, administer as soon as possible. If the missed dose of WINREVAIR is not administered within 3 days of the scheduled date, adjust the schedule to maintain 3-week dosing intervals. In case of an overdose, monitor for erythrocytosis [see Overdosage (10)].

2.3 Dosage Modifications Due to Hemoglobin Increase or Platelet Count Decrease

Check Hgb and platelet count before each dose for the first 5 doses, or longer if values are unstable. Thereafter, monitor Hgb and platelet count periodically [see Warnings and Precautions (5.1, 5.2)].

Delay treatment for at least 3 weeks if any of the following occur:

- Hgb increases >2.0 g/dL from the previous dose and is above ULN.
- Hgb increases >4.0 g/dL from baseline.
- Hgb increases >2.0 g/dL above ULN.
- Platelet count decreases to <50,000/mm^3 (<50 x 10^9/L).

Recheck Hgb and platelet count before reinitiating treatment. For treatment delays lasting >9 weeks, restart treatment at 0.3 mg/kg, and escalate to 0.7 mg/kg after verifying acceptable Hgb and platelet count.

2.4 Preparation and Administration

Administration is subject to monitoring of hemoglobin and platelet count [see Dosage and Administration (2.3), Warnings and Precautions (5.1, 5.2)].

WINREVAIR is intended for use under the guidance of a healthcare professional. Patients and caregivers may administer WINREVAIR when considered appropriate and when they receive training and follow-up from the healthcare provider (HCP) on how to reconstitute, prepare, measure, and inject WINREVAIR [see Patient Counseling Information (17)].

Confirm at subsequent visits that the patient and/or caregiver can correctly prepare and administer WINREVAIR, particularly if the dose changes or the patient requires a different kit [see Warnings and Precautions (5.1)].

Refer to the Instructions for Use (IFU) for detailed instructions on the proper preparation and administration of WINREVAIR.

Selecting the Appropriate Product Kit

If a patient’s body weight requires the use of two 45 mg vials or two 60 mg vials of lyophilized product, use a 2-vial kit instead of two individual 1-vial kits. A 2-vial kit includes instructions to combine the contents of two vials, which aids in measuring the proper dosage and eliminates the need for multiple injections [see How Supplied/Storage and Handling (16.1)].

Reconstitution Instructions

- Remove the injection kit from the refrigerator and wait 15 minutes to allow the prefilled syringe(s) and drug product to come to room temperature prior to preparation.
- Attach the vial adapter to the vial.
- Visually inspect the pre-filled syringe for any damage or leaks and the Sterile Water for Injection inside to ensure there are no visible particles.
- Snap off the cap of the pre-filled syringe and attach the syringe to the vial adapter.
- Inject all of the Sterile Water for Injection from the attached syringe into the vial containing the lyophilized powder. This will provide a final concentration of 50 mg/mL.
- Gently swirl the vial to reconstitute the drug product. DO NOT shake or vigorously agitate.
- Allow the vial to stand for up to 3 minutes to allow bubbles to disappear.
- Parenteral drug products should be inspected visually for particulate matter and discoloration prior to administration, whenever solution and container permit.
- When properly mixed, WINREVAIR should be clear to opalescent and colorless to slightly brownish-yellow and does not have clumps or powder.
- If prescribed a 2-vial presentation, repeat the steps within this section to prepare the second vial.
- Use the reconstituted solution as soon as possible, but no later than 4 hours after reconstitution. Discard unused reconstituted solution.

Syringe Preparation

- Turn the syringe and vial upside-down and withdraw the appropriate volume for injection, based on the patient’s weight.
  - If the dose amount requires the use of two vials, withdraw the entire contents of the first vial and slowly transfer full contents into the second vial.
  - Turn the syringe and vial upside-down and withdraw the required amount of drug product.
  - If necessary, remove excess drug product.
- If necessary, remove excess air from the syringe.

Administration Instructions

WINREVAIR is for subcutaneous injection.

- Select the injection site on the abdomen (at least 2 inches away from navel), upper thigh, or upper arm, and swab with an alcohol wipe. Select a new site for each injection that is not scarred, tender, or bruised.
  - For administration by the patient or caregiver, use only the abdomen and upper thigh (see IFU).
- Perform subcutaneous injection.

3 DOSAGE FORMS AND STRENGTHS

- For injection: 45 mg white to off-white lyophilized cake or powder appearance in a single-dose vial.
- For injection: 60 mg white to off-white lyophilized cake or powder appearance in a single-dose vial.

4 CONTRAINDICATIONS

None.

5 WARNINGS AND PRECAUTIONS

5.1 Erythrocytosis

WINREVAIR may increase hemoglobin. Severe erythrocytosis may increase the risk of thromboembolic events or hyperviscosity syndrome. In clinical studies, moderate elevations in Hgb (>2 g/dL above ULN) occurred in 15% of patients taking WINREVAIR while no elevations ≥4 g/dL above ULN were observed. Monitor Hgb before each dose for the first 5 doses, or longer if values are unstable, and periodically thereafter, to determine if dose adjustments are required [see Dosage and Administration (2.3), Adverse Reactions (6.1)].

5.2 Severe Thrombocytopenia

WINREVAIR may decrease platelet count. Severe thrombocytopenia may increase the risk of bleeding. In clinical studies, severe thrombocytopenia (platelet count <50,000/mm^3 [<50 x 10^9/L]) occurred in 3% to 6% of patients taking WINREVAIR. Thrombocytopenia occurred more frequently in patients also receiving prostacyclin infusion.

Do not initiate treatment if platelet count is <50,000/mm^3 [see Dosage and Administration (2.3)].

Monitor platelets before each dose for the first 5 doses, or longer if values are unstable, and periodically thereafter to determine whether dose adjustments are required. [see Dosage and Administration (2.3), Adverse Reactions (6.1)].

5.3 Serious Bleeding

In clinical studies, serious bleeding (e.g., gastrointestinal, intracranial hemorrhage) was reported in 4% vs 1% (STELLAR) and 7% vs 5% (ZENITH) of patients taking WINREVAIR vs placebo, respectively [see Clinical Studies (14.1)]. Patients with serious bleeding were more likely to be on prostacyclin background therapy and/or antithrombotic agents, or have low platelet counts. Advise patients about signs and symptoms of blood loss. Evaluate and treat bleeding accordingly. Do not administer WINREVAIR if the patient is experiencing serious bleeding [see Warnings and Precautions (5.2), Adverse Reactions (6.1)].

5.4 Embryo-Fetal Toxicity

Based on findings in animal reproduction studies, WINREVAIR may cause fetal harm when administered to a pregnant woman. In animal reproduction studies, administration of WINREVAIR to pregnant rats and rabbits during organogenesis resulted in adverse developmental outcomes, including increased embryo-fetal mortality, alterations to growth, and structural variations at exposures 4-fold and 0.6-fold (based on area under the curve [AUC]) those occurring at the maximum recommended human dose (MRHD), respectively. Advise pregnant women of the potential risk to a fetus. Advise females of reproductive potential to use an effective method of contraception during treatment with WINREVAIR and for at least 4 months after the final dose [see Use in Specific Populations (8.1, 8.3)].

5.5 Impaired Fertility

Based on findings in animals, WINREVAIR may impair female and male fertility. Advise patients on the potential effects on fertility [see Use in Specific Populations (8.3), Nonclinical Toxicology (13.1)].

6 ADVERSE REACTIONS

The following clinically significant adverse reactions are described elsewhere in the labeling:

- Erythrocytosis [see Warnings and Precautions (5.1)]
- Severe Thrombocytopenia [see Warnings and Precautions (5.2)]
- Serious Bleeding [see Warnings and Precautions (5.3)]
- Embryo-Fetal Toxicity [see Warnings and Precautions (5.4)]
- Impaired Fertility [see Warnings and Precautions (5.5)]

6.1 Clinical Trials Experience

Because clinical trials are conducted under widely varying conditions, adverse reaction rates observed in the clinical trials of a drug cannot be directly compared to rates in the clinical trials of another drug and may not reflect the rates observed in practice.

STELLAR

The following data reflect exposure to WINREVAIR in the STELLAR trial. Adult PAH patients with WHO FC II or III (n=323) were randomized in a 1:1 ratio to receive WINREVAIR or placebo in combination with background standard of care therapies. Patients received a starting dose of 0.3 mg/kg via SC injection and the dose was increased to the target dose of 0.7 mg/kg administered once every 3 weeks for 24 weeks. After completing the primary 24-week treatment phase, patients continued into a long-term double-blind (LTDB) treatment period, maintaining their randomized treatment assignment, until all patients completed the primary treatment period. The median duration of treatment was 273 days in the placebo group and 313 days in the WINREVAIR group [see Clinical Studies (14.1)].

The most common adverse reactions occurring in STELLAR (≥10% for WINREVAIR and at least 5% more than placebo) are shown in Table 3.

Table 3: Adverse Reactions ≥10% in Patients Receiving WINREVAIR and at least 5% More Than Placebo in STELLAR [Double-blind placebo-controlled period + Long-term double-blind period of STELLAR]
Adverse reaction | WINREVAIR N=163 | Placebo N=160
Headache | 40 (24.5) | 28 (17.5)
Epistaxis | 36 (22.1) | 3 (1.9)
Rash | 33 (20.2) | 13 (8.1)
Telangiectasia | 27 (16.6) | 7 (4.4)
Diarrhea | 25 (15.3) | 16 (10.0)
Dizziness | 24 (14.7) | 10 (6.3)
Erythema | 22 (13.5) | 5 (3.1)

Increased Hemoglobin

Increases in Hgb were managed by dose delays (10%), dose reductions (6%), or both (5%). Shifts in Hgb from normal to above normal levels occurred in 87 (53%) patients receiving WINREVAIR and in 23 (14%) patients receiving placebo.

Thrombocytopenia

Decreases in platelets were managed by dose delays (2%), dose reductions (2%), or both (2%). Shifts in platelet count from normal to below normal occurred in 40 (25%) patients receiving WINREVAIR and in 26 (16%) patients receiving placebo.

Telangiectasia

In patients exposed to WINREVAIR who experienced telangiectasia, the median time to onset was 36.1 weeks.

Increased Blood Pressure

In patients taking WINREVAIR, mean systolic/diastolic blood pressure increased from baseline by 2.2/4.9 mmHg at 24 weeks. In patients taking placebo, the change from baseline in mean blood pressure was -1.6/-0.6 mmHg.

Treatment Discontinuation

The incidences of treatment discontinuations due to an adverse reaction were 4% in the WINREVAIR group and 7% in the placebo group. No specific adverse reactions causing treatment discontinuations occurred with a frequency greater than 1% and more often in the WINREVAIR group.

ZENITH

The following data reflect exposure to WINREVAIR in the ZENITH trial. Adult PAH patients with WHO FC III or IV at high risk of mortality (n=172) were randomized in a 1:1 ratio to treatment with WINREVAIR or placebo in combination with background standard of care therapies. Patients who did not experience a primary endpoint event remained in the Double-Blind Placebo-Controlled (DBPC) Treatment Period, while patients who experienced an event of PAH worsening-related hospitalization of ≥24 hours were eligible to enroll into the open-label, long-term follow-up (LTFU) study SOTERIA. The median duration of exposure was longer in the WINREVAIR group (435 days) than in the placebo group (268 days) [see Clinical Studies (14.1)].

The overall incidences of adverse reactions in both arms were higher in the ZENITH trial than in the STELLAR trial. Severe reduction in platelet count <50,000/mm^3 (<50.0 x 10^9/L) occurred in 6% of patients taking WINREVAIR. In the WINREVAIR group, 1 patient (1%) discontinued study intervention due to an adverse event, compared with 4 patients (5%) in the placebo group.

Table 4: Adverse Reactions ≥10% in Patients Receiving WINREVAIR and at least 5% More Than Placebo in ZENITH
Adverse reaction | WINREVAIR N=86 | Placebo N=86
Infections | 58 (67.4) | 38 (44.2)
Epistaxis | 39 (45.3) | 8 (9.3)
Diarrhea | 22 (25.6) | 15 (17.4)
Telangiectasia | 22 (25.6) | 3 (3.5)
Increased hemoglobin | 13 (15.1) | 1 (1.2)
Rash | 9 (10.5) | 4 (4.7)
Erythema | 9 (10.5) | 3 (3.5)
Gingival bleeding | 9 (10.5) | 2 (2.3)

Uncontrolled Long-term Safety Data

PULSAR was a multicenter, randomized, double-blind, phase 2 trial that included a 24-week placebo-controlled treatment period, followed by an 18-month active-drug extension period. The safety profile in the long-term uncontrolled extension period of the PULSAR study was generally similar to that observed in the STELLAR study. Patients were treated with WINREVAIR 0.3 mg/kg or 0.7 mg/kg (n=104) and had a mean duration of exposure of 151 weeks (maximum 218 weeks).

Intrapulmonary Right-to-Left Shunting: Cases of intrapulmonary right-to-left shunting have been reported in a clinical trial with WINREVAIR. In SOTERIA, an ongoing open-label study of the long-term safety and efficacy of WINREVAIR, right-to-left intrapulmonary shunting has been reported in 2 participants (<0.5%) who developed worsening hypoxemia despite improved PAH hemodynamics. Post-marketing cases have also been reported.

Partial to complete improvement in oxygenation has been observed following discontinuation of WINREVAIR.

6.2 Post-marketing Experience

The following adverse reaction has been reported during post-approval use of WINREVAIR. Because these reactions are reported voluntarily from a population of uncertain size, it is generally not possible to reliably estimate their frequency or establish a causal relationship to drug exposure.

Cardiac disorders: pericardial effusion

8 USE IN SPECIFIC POPULATIONS

8.1 Pregnancy

Risk Summary

Based on findings in animal reproduction studies, WINREVAIR may cause fetal harm when administered to a pregnant woman. There are risks to the mother and the fetus associated with pulmonary arterial hypertension in pregnancy (see Clinical Considerations). There are no available data on WINREVAIR use in pregnant women to inform a drug-associated risk of major birth defects, miscarriage, or adverse maternal or fetal outcomes.

In animal reproduction studies, administration of WINREVAIR to pregnant rats and rabbits during the period of organogenesis resulted in adverse developmental outcomes, including embryo-fetal mortality, alterations to growth, and structural variations at exposures 4-fold and 0.6-fold (based on area under the curve [AUC]) above those occurring at the maximum recommended human dose (MRHD), respectively (see Data). Advise pregnant women of the potential risk to a fetus [see Use in Specific Populations (8.3)].

The background risk of major birth defects and miscarriage for the indicated population is not known. All pregnancies have a background risk of birth defect, loss, or other adverse outcomes. In the U.S. general population, the estimated background risk of major birth defects and miscarriage in clinically recognized pregnancies is 2% to 4% and 15% to 20%, respectively.

Report exposure during pregnancy or lactation to the Merck Sharp & Dohme, LLC Adverse Event reporting line at 1-877-888-4231.

Clinical Considerations

Disease-Associated Maternal and/or Embryo/Fetal Risk

In patients with pulmonary arterial hypertension, pregnancy is associated with an increased rate of maternal and fetal morbidity and mortality, including spontaneous abortion, intrauterine growth restriction, and premature labor.

Data

Animal Data

In embryo-fetal developmental toxicity studies, pregnant animals were dosed subcutaneously with sotatercept-csrk during the period of organogenesis. Sotatercept-csrk was administered to rats on gestation days 6 and 13 at doses of 5, 15, or 50 mg/kg and to rabbits on gestation days 7 and 14 at doses of 0.5, 1.5, or 5 mg/kg. Effects in both species included reductions in numbers of live fetuses and fetal body weights, delays in ossification, and increases in resorptions and post-implantation losses. In rats and rabbits, these effects were observed at exposures (based on area under the curve [AUC]) approximately 4-fold and 0.6-fold the maximum recommended human dose (MRHD), respectively. In rats only, skeletal variations (increased number of supernumerary ribs and changes in the number of thoracic or lumbar vertebrae) occurred at an exposure 15-fold the human exposure at the MRHD.

In a prenatal and postnatal development study in rats, sotatercept-csrk was administered subcutaneously at doses of 1.5 and 5 mg/kg on gestation days 6 and 13, or at dosages of 1.5, 5, or 10 mg/kg during lactation on days 1, 8, and 15. There were no adverse effects in first filial generation (F1) pups from dams dosed during gestation at estimated exposures up to 2-fold the MRHD. In F1 pups from dams dosed during lactation, decreases in pup weight correlated with delays in sexual maturation at estimated exposures (based on AUC) ≥2-fold the MRHD.

8.2 Lactation

Risk Summary

There are no data on the presence of sotatercept-csrk in human milk, the effects on the breastfed infant, or the effects on milk production. Because of the potential for serious adverse reactions in the breastfed child, advise patients that breastfeeding is not recommended during treatment with WINREVAIR, and for 4 months after the final dose.

8.3 Females and Males of Reproductive Potential

WINREVAIR may cause fetal harm when administered to pregnant women [see Use in Specific Populations (8.1)].

Pregnancy Testing

Pregnancy testing is recommended for females of reproductive potential before starting WINREVAIR treatment.

Contraception

Females

Advise female patients of reproductive potential to use effective contraception during treatment with WINREVAIR and for at least 4 months after the final dose if treatment is discontinued [see Use in Specific Populations (8.1)].

Infertility

Based on findings in animals, sotatercept-csrk may impair female and male fertility [see Nonclinical Toxicology (13.1)]. In male rats, although adverse histologic changes in reproductive organs were not reversible after a 13-week period, functional fertility demonstrated reversibility.

8.4 Pediatric Use

The safety and effectiveness of WINREVAIR have not been established in patients less than 18 years of age.

8.5 Geriatric Use

A total of 127 patients ≥65 years of age participated in clinical studies for PAH, of which 99 (78%) were treated with WINREVAIR. No differences in efficacy of WINREVAIR were observed between the <65-year-old and ≥65-year-old subgroups.

With the exception of bleeding events (a collective group of adverse events of clinical interest), there were no differences in safety between the <65-year-old and ≥65-year-old subgroups. Bleeding events occurred more commonly in the older WINREVAIR subgroup, but with no imbalance between age subgroups for any specific bleeding event.

Clinical studies of WINREVAIR did not include sufficient numbers of patients aged 75 and older to determine whether they respond differently from younger patients.

10 OVERDOSAGE

In healthy volunteers, WINREVAIR dosed at 1 mg/kg resulted in increases in Hgb associated with hypertension; both improved with phlebotomy. In the event of overdose, monitor closely for increases in Hgb and blood pressure, and provide supportive care as appropriate. WINREVAIR is not dialyzable.

11 DESCRIPTION

Sotatercept-csrk is a homodimeric recombinant fusion protein consisting of the extracellular domain of the human activin receptor type IIA (ActRIIA) linked to the human IgG1 Fc domain. The molecular weight based on the amino acid sequence of sotatercept-csrk is approximately 78 kDa as a homodimer.

Sotatercept-csrk for injection is a sterile, preservative-free, white to off-white lyophilized cake or powder appearance in single-dose vials for subcutaneous administration after reconstitution.

Each 45 mg single-dose vial provides 45 mg of sotatercept-csrk and citric acid monohydrate (0.40 mg), polysorbate 80 (0.18 mg), sodium citrate (1.84 mg), and sucrose (72 mg) at pH 5.8. After reconstitution with 1 mL Sterile Water for Injection, the resulting concentration is 50 mg/mL of sotatercept-csrk and the nominal deliverable volume is 0.9 mL.

Each 60 mg single-dose vial provides 60 mg of sotatercept-csrk and citric acid monohydrate (0.53 mg), polysorbate 80 (0.24 mg), sodium citrate (2.45 mg), and sucrose (96 mg) at pH 5.8. After reconstitution with 1.3 mL Sterile Water for Injection, the resulting concentration is 50 mg/mL of sotatercept-csrk and the nominal deliverable volume is 1.2 mL.

12 CLINICAL PHARMACOLOGY

12.1 Mechanism of Action

Sotatercept-csrk, a recombinant activin receptor type IIA-Fc (ActRIIA-Fc) fusion protein, is an activin signaling inhibitor that binds to activin A and other TGF- β superfamily ligands. As a result, sotatercept-csrk improves the balance between the pro-proliferative (ActRIIA/Smad2/3-mediated) and anti-proliferative (BMPRII/Smad1/5/8-mediated) signaling to modulate vascular proliferation. In rat models of PAH, a sotatercept-csrk analog reduced inflammation and inhibited proliferation of endothelial and smooth muscle cells in diseased vasculature. These cellular changes were associated with thinner vessel walls, partial reversal of right ventricular remodeling, and improved hemodynamics.

12.2 Pharmacodynamics

STELLAR

A greater decrease from baseline in pulmonary vascular resistance (PVR) was observed in the WINREVAIR group compared to the placebo group. The median treatment difference in PVR between sotatercept-csrk and placebo was -235 dynes*sec/cm^5 (95% CI: -288, -181). Sotatercept-csrk steady state exposure at 0.7 mg/kg dose was associated with near maximal reduction in PVR based on exposure-response analysis.
A greater decrease from baseline in NT-proBNP was observed in the WINREVAIR group compared to the placebo group. The median treatment difference in NT-proBNP between the sotatercept-csrk and placebo was -442 pg/mL (95% CI: -574, -310).

ZENITH

The median treatment difference in change in PVR from baseline between the sotatercept and placebo groups after 24 weeks was -340 dynes*sec/cm^5 (95% CI: -511, -168). The median treatment difference in change in NT-proBNP from baseline between the sotatercept-csrk and placebo groups after 24 weeks was -2339 pg/mL (95% CI: -3379, -1299). The median treatment difference in change from baseline in mean pulmonary artery pressure (mPAP) between the sotatercept-csrk and placebo groups after 24 weeks was -21.2 mm Hg (95% CI: -27.8, -14.6).

12.3 Pharmacokinetics

Following subcutaneous administration of 0.7 mg/kg WINREVAIR every three weeks to PAH patients (PULSAR, SPECTRA, and STELLAR), the steady state geometric mean (%CV) area under the time concentration curve (AUC) is 171.3 mcg×d/mL (34.2%), and peak concentration (Cmax) is 9.7 mcg/mL (30%). Sotatercept-csrk AUC and Cmax increased proportionally with dose. Steady state is achieved after approximately 15 weeks following initiation of multiple dosing. The accumulation ratio of sotatercept-csrk AUC is approximately 2.2. Sotatercept-csrk pharmacokinetics were similar in PAH participants in ZENITH.

Absorption

Following subcutaneous administration, the absolute bioavailability of sotatercept-csrk is approximately 66%. The sotatercept-csrk median time to peak drug concentration (Tmax) is approximately 7 days (range from 2 to 8 days) following multiple SC administration every 4 weeks.

Distribution

The population PK model estimated volume of distribution (%CV) of sotatercept-csrk at steady state is approximately 5.3 L (27.3%) in patients with PAH.

Elimination

The sotatercept-csrk effective half-life is approximately 24 days and its clearance is approximately 0.18 L/day.

Metabolism

Sotatercept-csrk is expected to be metabolized into small peptides by catabolic pathways.

Specific Populations

No clinically significant differences in sotatercept-csrk pharmacokinetics (PK) were observed based on age (18 to 81 years of age), sex, race, mild to moderate (eGFR ranging from 30 to 89 mL/min) renal impairment (PAH patients), or end-stage kidney disease (eGFR <15 mL/min) with dialysis. Based on limited data, severe renal impairment (eGFR ranging from 15 to 30 mL/min, n=3) had no impact on the PK of sotatercept-csrk. Sotatercept-csrk is not dialyzable. The effect of hepatic impairment on the PK of sotatercept-csrk has not been studied.

Body Weight

The clearance (CL) and central volume of distribution (Vc) increase with increase in body weight. This effect is not clinically significant when sotatercept-csrk is administered using weight-based dosing as recommended.

12.6 Immunogenicity

The observed incidence of anti-drug antibodies is highly dependent on the sensitivity and specificity of the assay. Differences in assay methods preclude meaningful comparisons of the incidence of anti-drug antibodies in the studies described below with the incidence of anti-drug antibodies in other studies, including those of WINREVAIR or of other sotatercept-csrk products.

During the 24-week treatment period in STELLAR, 27% (44/163) of sotatercept-csrk-treated patients developed anti-sotatercept-csrk antibodies (ADA). Among the 44 ADA-positive patients, 12 (27%) tested positive for neutralizing antibodies against sotatercept-csrk.

During the ZENITH trial, with a median sotatercept treatment duration of 435 days, 43% (36/84) of patients developed anti-sotatercept antibodies. Among these 36 patients, 20 (56%) tested positive for neutralizing antibodies against sotatercept.

There were no identified clinical effects of anti-sotatercept-csrk antibodies on pharmacokinetics, pharmacodynamics, safety, or effectiveness of sotatercept-csrk over the treatment duration of 24 weeks at the recommended dosage in these studies.

13 NONCLINICAL TOXICOLOGY

13.1 Carcinogenesis, Mutagenesis, Impairment of Fertility

No carcinogenicity or mutagenicity studies have been conducted with sotatercept-csrk.

In a fertility and early embryonic development study in female rats, sotatercept-csrk was administered SC once weekly at doses of 5, 15, and 50 mg/kg beginning 2 weeks prior to mating and through gestation day 7. At doses ≥15 mg/kg (≥9 fold the MRHD, based on estimated AUC), pregnancy rates were decreased and there were increases in preimplantation and postimplantation loss and reductions in live litter size. Increased estrous cycle duration occurred at 50 mg/kg only (21-fold the MRHD, based on estimated AUC).

In a fertility study in male rats, sotatercept-csrk was administered SC once weekly at doses of 0.3, 3, and 30 mg/kg for 13 weeks (beginning 10 weeks prior to mating). A subset of animals was examined after a 13-week recovery period. At ≥0.3 mg/kg (0.5-fold the MRHD, based on estimated AUC) there were non-reversible histologic changes in the efferent ducts, testes, and epididymides. Reversible decreases in functional fertility endpoints occurred at 30 mg/kg (20-fold the MRHD, based on estimated AUC).

14 CLINICAL STUDIES

14.1 Pulmonary Arterial Hypertension

STELLAR

The efficacy of WINREVAIR was evaluated in adult patients with PAH in the STELLAR trial (NCT04576988). STELLAR was a global, double-blind, placebo-controlled, multicenter, parallel-group clinical trial in which 323 patients with PAH (WHO Group 1, FC II or III) were randomized 1:1 to WINREVAIR (target dose 0.7 mg/kg) (n=163) or placebo (n=160) administered subcutaneously once every 3 weeks.

Participants were: 79% female; had a median age of 48 years (range: 18 to 82 years), and median body weight of 68 kg (range 38 to 141 kg); and 89% White, 2% Black/African American, 2% Asian, 0.3% American Indian or Alaska Native, 0.3% Native Hawaiian or Other Pacific Islander, 6% Missing/Other races. The most common PAH etiologies were idiopathic PAH (59%), heritable PAH (18%), and PAH associated with connective tissue diseases (CTD) (15%). STELLAR excluded patients with human immunodeficiency virus (HIV)-associated PAH, PAH associated with portal hypertension, schistosomiasis-associated PAH, and pulmonary veno occlusive disease. The mean time from PAH diagnosis to screening was 8.8 years. Most participants were receiving either three (61%) or two (35%) background drugs for PAH, and 40% were receiving prostacyclin infusions. Patients had a WHO FC II (49%) or III (51%) at baseline.

The primary efficacy endpoint was the change from baseline at Week 24 in 6-Minute Walk Distance (6 MWD). In the WINREVAIR group, the placebo-adjusted median increase in 6 MWD was 41 meters (95% CI: 28, 54; p<0.001). Figure 1 displays placebo-adjusted changes in 6 MWD at Week 24 in relevant subgroups.

Figure 1: Change from Baseline in 6-Minute Walk Distance (meters) at Week 24 in Subgroups in STELLAR

*Hodges-Lehmann location shift from placebo estimate (median of all paired differences). ASE = asymptotic standard error.
Change from baseline in 6 MWD at Week 24 for subjects who died was imputed to -2000 meters to receive the worst rank. Change from baseline in 6 MWD at Week 24 for subjects who had missing data due to a non-fatal clinical worsening event was imputed to -1000 meters to receive the next-worst rank.

Treatment with WINREVAIR led to an improvement from baseline by at least 1 WHO FC at Week 24 in 29% of patients compared to 14% of patients treated with placebo (p<0.001).

Treatment with WINREVAIR resulted in an 84% reduction in the occurrence of death from any cause or PAH clinical worsening events compared to placebo (see Table 5 and Figure 2). These outcomes were captured until the last patient completed the Week 24 visit (data up to the data cutoff; median duration of exposure 33.6 weeks).

Table 5: Death from Any Cause or PAH Clinical Worsening Events in STELLAR
 | WINREVAIR (N=163) n (%) | Placebo (N=160) n (%) | Hazard Ratio (95% CI)
Number of subjects who experienced death or at least one clinical worsening event | 9 (5.5) | 42 (26.3) | 0.16 (0.08, 0.35) p<0.001
Assessment of clinical worsening events [A subject can have more than one assessment recorded for their clinical worsening.]
Death | 2 (1.2) | 7 (4.4)
Worsening-related listing for lung and/or heart transplant | 1 (0.6) | 2 (1.3)
Need to initiate rescue therapy with an approved PAH therapy or the need to increase the dose of infusion prostacyclin by 10% or more | 2 (1.2) | 17 (10.6)
Need for atrial septostomy [There were no events of atrial septostomy.] | 0 (0.0) | 0 (0.0)
PAH-specific hospitalization (≥24 hours) | 0 (0.0) | 8 (5.0)
Deterioration of PAH [Deterioration of PAH is defined by both of the following events occurring at any time, even if they began at different times, as compared to their baseline values: (a) Worsened WHO functional class (II to III, III to IV, II to IV, etc.); and (b) Decrease in 6 MWD by ≥15% (confirmed by two 6 MWTs at least 4 hours apart but no more than one week).] | 4 (2.5) | 15 (9.4)
N = number of subjects in the category.
6 MWT = 6-Minute Walking Test

Figure 2: Time to Death from Any Cause or First Occurrence of PAH Clinical Worsening Event Kaplan-Meier Plot in STELLAR

ZENITH

The efficacy of WINREVAIR was evaluated in adult PAH patients with WHO FC III or IV at high risk of mortality in the ZENITH trial (NCT04896008). ZENITH was a global, double-blind, placebo-controlled, multicenter, parallel-group clinical trial in which 172 patients were randomized 1:1 to WINREVAIR (target dose 0.7 mg/kg) (n=86) or placebo (n=86) administered subcutaneously once every 3 weeks. Efficacy was evaluated at the pre-specified interim analysis which occurred when 61 patients experienced a primary endpoint event and median patient time on study was 273 days.

The demographic and baseline clinical characteristics were similar between the WINREVAIR and placebo groups. Participants were: 77% female; had a median age of 58 years (range: 18 to 75 years); and 87% White, 5% Black/African American, 4% Asian, 1% American Indian or Alaska Native, 3% Missing/Other race, 74% were FC III and 26% were FC IV. The most common PAH etiologies were idiopathic PAH (50%), PAH associated with connective tissue diseases (CTD) (28%), and heritable PAH (11%). The mean time since PAH diagnosis to screening was 8 years. Participants were on background PAH treatment, 72% on triple therapy, 28% on double therapy, and 59% on prostacyclin infusion therapy. The REVEAL Lite 2 risk score was <9 for 2% of participants, 9 to 10 for 67% of participants, and ≥11 for 30% of participants. The ZENITH trial excluded patients diagnosed with human immunodeficiency virus (HIV)-associated PAH, PAH associated with portal hypertension, pulmonary veno-occlusive disease, or pulmonary capillary hemangiomatosis or overt signs of capillary and/or venous involvement.

The primary efficacy endpoint was time to first event of all-cause death, lung transplantation, or PAH worsening-related hospitalization of ≥24 hours. In the WINREVAIR treatment group, the risk of a first event of all-cause death, lung transplantation, or PAH worsening-related hospitalization of ≥24 hours was 76% lower compared with the placebo group (HR: 0.24; 95% CI: 0.13, 0.43; p<0.0001) (see Table 6). Fewer participants in the WINREVAIR group (15 [17%]) than in the placebo group (47 [55%]) had a primary endpoint event as of the data cutoff. Based on the primary endpoint result, the study was stopped for favorable efficacy at the interim analysis.

The treatment effect of WINREVAIR was consistent across the prespecified subgroups (see Figure 4).

Table 6: Primary Endpoint Results in ZENITH
 | WINREVAIR (N=86) n (%) | Placebo (N=86) n (%) | Hazard Ratio (95% CI) p-value
Number of participants with at least 1 primary event [The primary composite endpoint analysis includes the first occurrence of an adjudicated morbidity-mortality event up to the data cutoff. All deaths up to the data cutoff are included, regardless of adjudication and regardless of whether they occurred during or post-ZENITH, except for those occurring after lung transplantation or enrollment in SOTERIA.] | 15 (17.4) | 47 (54.7) | 0.24 (0.13, 0.43) <0.0001
Components of primary endpoint [Shows each component of the composite primary endpoint as a standalone outcome. A participant is included in more than one row if multiple events meeting primary endpoint definition were observed.]
All-cause death | 7 (8.1) | 13 (15.1)
Lung transplantation | 1 (1.2) | 6 (7.0)
PAH worsening-related to hospitalization (≥24 hours) | 8 (9.3) | 43 (50.0)

Figure 3: Time to First Event in ZENITH of All-cause Death, Lung Transplantation, or PAH Worsening-related Hospitalization of ≥ 24 Hours Kaplan-Meier Plot

Figure 4: Hazard Ratio for the Primary Endpoint in Subgroups in ZENITH

Subgroup analyses were not displayed if the number of participants in subgroup category was less than 10% of FAS.
For participants with REVEAL Lite 2.0 risk score <9 at screening, they were grouped under “9 to 10” for the analyses.

The secondary endpoint of overall survival (OS) included all deaths up to the data cutoff, except for those occurring after lung transplantation or enrollment in a long-term follow-up study. Twenty OS events were observed (7 deaths in the WINREVAIR treatment group and 13 deaths in the placebo group). The point estimate for the OS HR favored the WINREVAIR treatment group over the placebo group.

Subsequent secondary endpoints were not eligible to be tested due to the hierarchical testing strategy.

16 HOW SUPPLIED/STORAGE AND HANDLING

16.1 How Supplied

WINREVAIR (sotatercept-csrk) for injection is a white to off-white lyophilized cake or powder appearance supplied in single-dose vials (45 mg or 60 mg) packaged in kits that contain one measuring syringe and one safety needle. Each kit also contains Sterile Water for Injection in prefilled syringes necessary to reconstitute the product, vial adapter(s), and alcohol pads, as shown in Table 7.

Table 7: Kit Contents
Kit | Vial Adapters | Alcohol Pads | Sterile Water for Injection in prefilled syringes | NDC
(1) 45 mg vial | 1 | 4 | (1) 1 mL syringe | NDC # 0006-5090-01
(1) 60 mg vial | 1 | 4 | (1) 1.3 mL syringe | NDC # 0006-5091-01
(2) 45 mg vials | 2 | 8 | (2) 1 mL syringes | NDC # 0006-5087-01
(2) 60 mg vials | 2 | 8 | (2) 1.3 mL syringes | NDC # 0006-5088-01

16.2 Storage and Handling

Store vials refrigerated at 2°C to 8°C (36°F to 46°F) in original carton to protect from light. Do not freeze.

The kit should remain in the refrigerator until ready for use. The unused kit can be out of the refrigerator for (up to 25°C/77°F) up to 24 hours. For additional information on temperature excursions, call Merck Sharp & Dohme LLC at 1-800-672-6372.

17 PATIENT COUNSELING INFORMATION

Advise patients to read the FDA-approved patient labeling (Patient Information and IFU).

Discuss the following with patients prior to and during treatment with WINREVAIR.

Erythrocytosis

Caution patients that WINREVAIR may raise Hgb to levels that increase their risk of thrombotic events. Inform patients that Hgb levels will be assessed before at least the first 5 doses and then periodically, as dosage may need to be adjusted [see Warnings and Precautions (5.1)].

Severe Thrombocytopenia

Caution patients that WINREVAIR may cause platelet count to decrease, which if severe could cause bleeding. Inform patients that platelet count will be assessed before at least the first 5 doses and then periodically, as dosage may need to be adjusted [see Warnings and Precautions (5.2)].

Serious Bleeding

Inform patients of the possibility of serious bleeding, which is more likely to occur if they have low platelet counts or while on prostacyclin background therapy and/or antithrombotic agents. Advise patients to notify their healthcare provider about signs and symptoms of bleeding [see Warnings and Precautions (5.3)].

Embryo-Fetal Toxicity

Advise females of reproductive potential of the potential risk to a fetus. Advise females of reproductive potential to use effective contraception while receiving WINREVAIR and for at least 4 months after the final dose. Advise females to contact their healthcare provider if they become pregnant, or if pregnancy is suspected during treatment with WINREVAIR [see Warnings and Precautions (5.4), Use in Specific Populations (8.1)]. Report exposure during pregnancy or lactation to the Merck Sharp & Dohme, LLC Adverse Event reporting line at 1-877-888-4231.

Lactation

Advise females not to breastfeed during treatment with WINREVAIR and for 4 months after the final dose [see Use in Specific Populations (8.2)].

Females and Males of Reproductive Potential

Advise females and males of reproductive potential that WINREVAIR may impair fertility [see Use in Specific Populations (8.3), Nonclinical Toxicology (13.1)].

Administration by Patient or Caregiver

Review the IFU with the patient or caregiver step-by-step. Provide training to the patient or caregiver regarding proper preparation and administration of WINREVAIR and decide whether a patient or caregiver is capable of preparing and administering WINREVAIR independently [see Dosage and Administration (2.4)].

Make sure the patient or caregiver can do the following correctly:

- reconstitute the medicine,
- measure the correct amount of medicine according to the patient’s prescription,
- select and prepare a proper injection site, and
- inject the medicine subcutaneously.

Incorrect Dose or Missed Dose

Inform patients to call their healthcare provider for further instruction if they take more than or less than the correct dose. Advise them about signs/symptoms to monitor for and what to do if any of these signs/symptoms should occur. Advise them that additional laboratory tests may be required prior to the next scheduled dose to ensure that the next dose can be safely administered.

Instruct the patient that if they miss the prescribed dose of WINREVAIR, they should take it within 3 days and maintain the original schedule for the next dose. If not taken within 3 days, instruct them to call their healthcare provider for guidance [see Dosage and Administration (2.2)].

Manufactured by:
Merck Sharp & Dohme LLC, Rahway, NJ 07065, USA

U.S. license number 0002

For patent information: www.msd.com/research/patent

Copyright © 2024-2025 Merck & Co., Inc., Rahway, NJ, USA, and its affiliates.
All rights reserved.

uspi-mk7962-i-2512r004

PATIENT INFORMATION
WINREVAIR™ (WIN-reh-vair)
(sotatercept-csrk)
for injection, for subcutaneous use

What is WINREVAIR?

WINREVAIR is a prescription medicine used to treat adults with pulmonary arterial hypertension (PAH). PAH is a type of high blood pressure in the arteries of your lungs.

WINREVAIR can:

- improve your ability to exercise and perform normal activities with fewer symptoms, and
- reduce the risk of your physical condition and symptoms worsening, including lowering your risk of hospitalization for PAH, lung transplant, and death.

It is not known if WINREVAIR is safe and effective in children under 18 years of age.

What should I tell my healthcare provider before taking WINREVAIR?

- Tell your healthcare provider about:
  - All of your medical conditions
  - All of the medicines you take, including prescriptions and over-the-counter medicines, vitamins, or herbal supplements

If you are able to get pregnant:

- WINREVAIR may harm your unborn baby. Tell your healthcare provider if you are pregnant or planning to get pregnant.
- Tell your healthcare provider right away if you become pregnant or think you may be pregnant during treatment with WINREVAIR.
- Your healthcare provider should do a pregnancy test before you start taking WINREVAIR.
- You should use effective birth control during treatment with WINREVAIR and for at least 4 months after your final dose. Ask your healthcare provider about birth control methods that may be right for you.
- You or your healthcare provider should report any exposure to WINREVAIR during pregnancy by calling 1-877-888-4231.

If you are breastfeeding or planning to breastfeed:

- Tell your healthcare provider if you are breastfeeding or planning to breastfeed. It is not known if WINREVAIR passes into breast milk.
- Do not breastfeed during treatment with WINREVAIR and for 4 months after your final dose. Talk to your healthcare provider about the best way to feed your baby.
- You or your healthcare provider should report any exposure to WINREVAIR during breastfeeding by calling 1-877-888-4231.

Before you take WINREVAIR:

- If your healthcare provider decides that you or a caregiver can give your injections of WINREVAIR at home, you or your caregiver should receive training from your healthcare provider on the right way to prepare and inject WINREVAIR. Do not try to inject WINREVAIR until you have been shown how to inject WINREVAIR by your healthcare provider.
- Your healthcare provider will do a blood test before your first 5 doses of WINREVAIR, longer if needed, and then from time to time to check your levels of hemoglobin (a protein in red blood cells that carries oxygen) and platelets (blood cells that help blood clot). After each of these blood tests, your healthcare provider may delay treatment or change your dose if needed.
- See the detailed “Instructions for Use” booklet that comes with WINREVAIR for information on how to prepare and inject a dose of WINREVAIR.

How should I take WINREVAIR?

- Use WINREVAIR exactly as your healthcare provider tells you to.
- You will give WINREVAIR every 3 weeks as an injection just under your skin (subcutaneous) in your:
  - stomach (abdomen) at least 2 inches away from the belly button, or
  - upper thigh
- You should inject WINREVAIR right away after mixing the medicine powder with the sterile water for injection, but no later than 4 hours after mixing.

Your prescribed dose:

- Your healthcare provider will tell you how much WINREVAIR to inject and when to inject it. This is because your prescribed dose depends on your body weight and blood tests.
- Do not change your dose or stop taking WINREVAIR without talking to your healthcare provider.
- Do not take WINREVAIR more often than your healthcare provider tells you to. If you are not sure when to take WINREVAIR, call your healthcare provider.
- Your healthcare provider may delay treatment, change your dose, or stop treatment depending on how you respond to WINREVAIR.

What if I take the wrong dose or miss my dose?

- If you give more than or less than your prescribed dose, call your healthcare provider right away.
- If you miss your dose of WINREVAIR:
  - If it has been 3 days or fewer, give it as soon as possible. You can then follow your usual schedule for your next dose.
  - If it has been more than 3 days, call your healthcare provider for what to do.

What are the possible side effects of WINREVAIR?

WINREVAIR may cause serious side effects including:

- High level of hemoglobin in your blood. High levels of hemoglobin are common with WINREVAIR and can be severe and increase your risk for blood clots. Your healthcare provider will do blood tests to check your hemoglobin levels before starting and regularly during treatment with WINREVAIR.
- Severely low number of platelets in your blood. Low platelet counts are common with WINREVAIR and can be severe and increase your risk of bleeding. Your healthcare provider will do blood tests to check your platelet levels before starting and regularly during treatment with WINREVAIR. Tell your healthcare provider if you develop easy bruising or bleeding, bleeding that does not stop, or nosebleeds.
- Serious bleeding. You are more likely to have serious bleeding if you have low platelet counts, take prostacyclin medicines to treat PAH, or take medicines to help keep blood clots from forming. Tell your healthcare provider if you develop any signs or symptoms of bleeding, including:

- vomiting blood or your vomit looks like coffee-grounds
- pink or brown urine
- red or black stools that look like tar
- coughing up blood or blood clots
- persistent headaches

- nausea
- dizziness or feeling weak
- persistent abdominal cramps
- severe back pain
- abnormally heavy menstrual bleeding

- Decreased fertility. WINREVAIR may affect female and male fertility, which may affect your ability to have children. Talk to your healthcare provider if this is a concern for you.

The most common side effects of WINREVAIR include:

- infections
- headache
- nose bleeds
- rash
- tiny blood vessels that look like pink or red lines on the skin (spider veins)

- diarrhea
- dizziness
- redness
- bleeding gums

These are not all the possible side effects of WINREVAIR.

Call your doctor for medical advice about side effects. You may report side effects to FDA at 1-800-FDA-1088.

How should I store WINREVAIR?

- Store WINREVAIR in the refrigerator at 36°F to 46°F (2°C to 8°C). Do not freeze.
- Store in the original carton to protect from light.

Keep WINREVAIR and all medicines out of the reach of children and pets.

General information about the safe and effective use of WINREVAIR.

Medicines are sometimes prescribed for purposes other than those listed in a Patient Information leaflet. Do not use WINREVAIR for a condition for which it was not prescribed. Do not give WINREVAIR to other people, even if they have the same symptoms that you have. It may harm them. You can ask your pharmacist or healthcare provider for information about WINREVAIR that is written for healthcare professionals.

What are the ingredients in WINREVAIR?
Active ingredient: sotatercept-csrk
Inactive ingredient(s): citric acid monohydrate, polysorbate 80, sodium citrate, and sucrose.

Manufactured by: Merck Sharp & Dohme LLC, Rahway, NJ 07065, USA.
US License Number 0002
For patent information: www.msd.com/research/patent
Copyright © 2024-2025 Merck & Co., Inc., Rahway, NJ, USA, and its affiliates.
All rights reserved.
usppi-mk7962-i-2510r001
For more information, call 1-877-888-4231, or go to www.WINREVAIR.com.

This Patient Information has been approved by the U.S. Food and Drug Administration

Revised: October 2025

INSTRUCTIONS FOR USE

Important: Read this booklet first | Important
INSTRUCTIONS FOR USE | Mix
WINREVAIR™ (WIN-reh-vair) (sotatercept-csrk) for injection, for subcutaneous use How to use your WINREVAIR injection kit | Withdraw
For package containing 1 vial For subcutaneous injection only (inject directly under the skin) | Inject

In this booklet:

Before you start

Important information for patients or caregivers

Get to know the parts of your kit

Important information you need to know before injecting WINREVAIR

Storing your injection kit

Get started

Mix powdered medicine into liquid form

Withdraw your prescribed dose

Inject your medicine

How to throw away WINREVAIR

Frequently asked questions

Before you start:

Read this booklet
Read this Instructions for Use from start to finish before using WINREVAIR and each time you get a refill. There may be new information.

Start with your healthcare provider
Do not use WINREVAIR until your healthcare provider has shown you or your caregiver the right way to prepare and inject it. Your healthcare provider should show you how to inject WINREVAIR before you use it for the first time.

Questions?
If you have questions about how to give WINREVAIR the right way or need more information, call your pharmacy or healthcare provider.
For general product information visit www.WINREVAIR.com or call Merck Sharp & Dohme LLC at 1-800-672-6372.

Important information for patients or caregivers

Before you prepare and inject WINREVAIR, you must be:

- trained by a healthcare provider following this Instructions for Use booklet step-by-step, and
- capable of independent administration of WINREVAIR as determined by a healthcare provider

Before using WINREVAIR, make sure you are trained to do the following correctly:

1. Reconstitute (mix) the medicine
2. Measure the correct amount of medicine according to your prescription
3. Select and prepare a proper injection site
4. Inject the medicine subcutaneously

Get to know the parts of your kit

Top Tray

Use to mix the medicine

1 Vial of WINREVAIR medicine powder

1 Prefilled syringe with sterile water for injection to mix medicine powder into liquid form

1 Vial adapter to connect the vial and syringe

Bottom Tray

Use to inject the medicine

Needle for injection

Empty dosing syringe to measure, withdraw, and inject your medicine

Important information you need to know before injecting WINREVAIR

- You must mix WINREVAIR before using it. Make sure the medicine powder in the vial is completely dissolved before you inject.
- Check your prescribed dose (amount in ‘mL’) each time you use WINREVAIR. Your prescribed dose may change. Your prescribed dose is on the prescription label on your kit.
- Use only the supplies that are in the kit to prepare your prescribed dose.
- Do not open the package or mix the medicine until you are ready to use it.
- Do not reuse any of the supplies. After your injection, throw away the used vials with any remaining WINREVAIR medicine, needle, caps, and syringes in a sharps container. See pages 36-37 for more information.

Storing your injection kit

Store WINREVAIR injection kit in the refrigerator at 36°F to 46°F (2°C to 8°C). Do not freeze.

Store in the original carton to protect from light.

Keep injection kit out of the reach of children and pets.

Get started

Before you can prepare and inject WINREVAIR, you must first be trained and determined to be capable of independent administration of WINREVAIR by a healthcare provider.

1 Check WINREVAIR injection kit and expiration date

Remove the WINREVAIR injection kit from the refrigerator.

Check the expiration date and look for any signs of damage on the kit or on the supplies.
If expired or damaged, do not use.
Call your pharmacy to get a new kit.

Check that you have the medicine that your healthcare provider prescribed.

2 Let your kit come to room temperature, gather supplies, and wash your hands

Wait 15 minutes to allow your kit to warm to room temperature.
Cold medicine is more painful to inject.

Along with your kit, gather these items and find a clean, flat surface where you will prepare and inject your dose.

Sharps disposal container

Gauze, cotton ball, or bandage

Wash your hands with soap and water.

Mix powdered medicine into liquid form

Start with the Top Tray

3 Remove medicine vial, prefilled syringe with sterile water for injection, alcohol wipes, and vial adapter from the kit.

4a Check medicine vial

Check the vial label to confirm the medicine is not expired.

Inspect the medicine powder.
It should be white to off-white.

Do not use if expired, damaged, discolored, or you can see particles in it.

4b Remove plastic cap and clean vial

Flip off the plastic cap and clean the rubber stopper on top of the vial with an alcohol wipe.

Do not use if vial cap is missing.

Do not touch the cleaned rubber stopper.

Set vial aside on a clean, flat surface.

5a Align vial adapter to vial

Peel open the vial adapter package and remove vial adapter from its package. | Hold the blue neck of the vial adapter and align the vial adapter on top of the vial. Do not touch the inside of the vial adapter.

5b Attach vial adapter to vial

Hold the vial with one hand. Push down firmly so it snaps in place (you may feel some resistance).

5c Clean vial adapter

Clean the top of the vial adapter with an alcohol wipe.

6 Check prefilled syringe

Confirm the sterile water inside the prefilled syringe is clear and the product is not expired or leaking.
Do not use if you see any clumps, particles, discoloration, or product is expired. You might see air bubbles. This is okay.

7 Snap off prefilled syringe white cap

Snap off the prefilled syringe cap along the perforation.

8 Connect prefilled syringe to vial adapter

Pick up the vial with the vial adapter attached.
Align the prefilled syringe tip on the blue circle of the vial adapter.

Push then twist the prefilled syringe onto the vial adapter until you cannot turn further. While twisting, be sure to hold onto the vial adapter.

9 Transfer sterile water from prefilled syringe to vial

Slowly push the plunger all the way down to transfer all the sterile water into the vial (the plunger will move up; this is normal).

10 Swirl to mix medicine

Do not shake the vial. Hold the prefilled syringe and gently swirl the vial in a circular motion until the powder is fully dissolved. This may take up to 2 minutes. | When the medicine is mixed well, it should be clear. If not, repeat this step until it is clear. | Press the plunger down to make sure all the liquid is in the vial (the plunger will move up; this is normal).

11 Wait for large bubbles in the vial to go away

It is okay to have slight foam around edges of the vial | Set vial aside for large bubbles to go away. This may take up to 3 minutes.

12 Prepare vial by removing extra air

With the vial standing upright, gently pull the plunger upwards to the top of the barrel. Do not to pull the plunger out of the syringe.
Note: Pulling extra air out of the vial will help to make sure you have the right dose.

13 Remove prefilled syringe from vial

Hold the vial adapter and unscrew the prefilled syringe from the vial. Throw away the prefilled syringe in the sharps container. | You should have a vial of medicine prepared and ready to be used in the next steps.

Withdraw your prescribed dose

For the next steps, you will need:

1. Mixed vial of medicine
2. Items from the Bottom Tray (needle, dosing syringe for injection, and alcohol wipes).

14 Clean top of vial adapter

With a new alcohol wipe from the bottom tray, clean the top of the vial adapter.

15 Remove empty dosing syringe from its package

Find the empty dosing syringe in the bottom tray and remove it from its package.

You will use this dosing syringe to measure out the medicine you need (based on your prescribed dose).

16 Pull air into the dosing syringe

You must do this to make sure pressure in the vial is even and you get an accurate dose.

Hold the dosing syringe upright and pull down the plunger to draw air into the dosing syringe. Stop when top rim of plunger is at the amount in ‘mL’ that matches your prescribed dose. Your prescribed dose is on the prescription label on your kit.

17 Connect dosing syringe to the vial

While holding the vial adapter, push then twist the dosing syringe onto the vial adapter until it stops.

18 Push air into vial, then flip vial upside down

Push the plunger all the way down to transfer all the air into the vial.
Then hold the plunger in place with your thumb and flip the vial upside down.

19 Pull plunger back to withdraw your prescribed dose

With the vial and dosing syringe upside down, slowly pull the plunger back.
Stop when you get to the amount in ‘mL’ that matches your prescribed dose.

20 Check for large air bubbles and air pockets

Check to see if there are large air bubbles or an air pocket in the syringe. You will remove extra air in the next steps.

21 Remove air bubbles and air pockets from syringe

If you see large air bubbles or an air pocket, tap the side of the dosing syringe to move the air to the top.

Slowly push the plunger up to remove extra air.

22 Compare amount to prescribed dose

After removing all extra air, compare the amount in your syringe to your prescribed dose.
If you do not have your prescribed dose in your syringe, slowly pull the plunger back again to withdraw more medicine from the vial.
Repeat Steps 19 to 21 until you get your prescribed dose and no large bubbles or air pockets remain.

23 Confirm your prescribed dose

Before you continue, check to make sure you have the prescribed dose in the dosing syringe.
If the amount does not match your prescribed dose, repeat Steps 19 to 22.

24 Remove the dosing syringe from the vial and set dosing syringe aside

Hold the plunger in place with one hand. With the other hand, hold the vial adapter and unscrew the filled dosing syringe from the vial.

Throw away the used vial into the sharps container.

Place the filled dosing syringe on a clean, flat surface.
Do not touch the dosing syringe tip or let it to touch any surfaces.

25 Attach injection needle

Find the needle in the bottom tray and open its package. | With the needle still in the package, grip the base of the needle and twist on the dosing syringe until it stops. Remove the needle package. | Move the safety shield away from the needle and toward the syringe. Place the dosing syringe on a clean, flat surface. Do not uncap the needle.

26 Choose and clean your injection site

Select an injection site on your stomach (abdomen) or your upper thigh. If injecting on your stomach, avoid a 2-inch area around your belly button.
Choose a different site every time you inject.
Do not inject into skin that is damaged, sore, tender, bruised, or has red patches.
Do not inject through clothes.

Clean the injection site with a new alcohol wipe.
Do not touch the cleaned injection site again.

Now, you are ready to inject the medicine.

Inject your medicine

27 Inject your medicine

Pull the cap straight off the needle. Throw away the cap. Do not touch the plunger until ready to inject so you do not lose any medicine. | Gently pinch and hold a fold of skin where you will inject. Insert the needle with a dartlike motion at a 45° to 90° angle. | Push the plunger with slow, steady pressure all the way down until the dosing syringe is empty. Confirm all the medicine has been injected. You can let go of the skin fold now.

Keep your fingers away from the needle at all times.
While keeping the plunger pushed in, remove the needle from your skin at the same angle you inserted it. | To reapply the safety shield, push the shield against a flat surface until you hear a “click” and see that the needle is covered. | Throw away the dosing syringe and used items in a sharps disposal container. Do not remove the needle from the dosing syringe.

How to throw away WINREVAIR

- Throw away any used vials (including any remaining WINREVAIR liquid), needle, vial and needle caps, and used syringes in an FDA-cleared sharps disposal container.
- Do not throw away the WINREVAIR vials, syringes, or needle in your household trash.
- Do not reuse any of the supplies. WINREVAIR is for one time use only.
- Important: Always keep the sharps disposal container out of reach of children and pets.

If you do not have an FDA-cleared sharps disposal container, you may use a household container that is:

- made of a heavy-duty plastic,
- can be closed with a tight-fitting, puncture-resistant lid, without sharp objects being able to come out,
- upright and stable during use,
- leak resistant, and
- properly labeled to warn of hazardous waste inside the container.

When your sharps disposal container is almost full, you will need to follow your community guidelines for the right way to throw away your sharps disposal container. There may be state or local laws about how you should throw away used needles, dosing syringes, and prefilled syringes.

For more information about safe sharps disposal, and for specific information about sharps disposal in the state that you live in, go to the FDA’s website at: http://www.fda.gov/safesharpsdisposal.
Do not recycle your used sharps container.

Frequently asked questions

What should I do if I am bleeding at the injection site?

Place a cotton ball or bandage on your skin right away and apply a small amount of pressure. If the bleeding does not stop, call your healthcare provider right away.

Where can I find my prescribed dose?

Your prescribed dose in ‘mL’ is on your prescription label on your kit. Contact your healthcare provider if you cannot find your prescribed dose.

What should I do if I accidentally get some medicine on my skin or my work surface?

Wash the area thoroughly with soap and water right away.

What should I do if I am not sure I administered my prescribed dose correctly?

Call your pharmacy or healthcare provider.

What should I do if the plunger of my dosing syringe moves automatically when I try to withdraw medicine from the vial?

Do not worry if your plunger moves slightly on its own when you are filling your dosing syringe with medicine.

With one hand, hold the plunger in place to stop the plunger from moving. With the other hand, unscrew the vial from the dosing syringe.

After unscrewed, it is safe to let go of the plunger.

You can avoid this automatic plunger movement by pushing air into the vial before filling your dosing syringe with medicine. Refer to Steps 16 to 23 for detailed instructions.

What should I do if my kit parts are damaged or are discolored, cloudy, or have particles?

Do not use your kit. Call your pharmacy to get a new kit.

What should I do if my medicine does not turn clear after mixing and swirling?

Do not use the medicine if you have swirled the medicine vial for about 2 minutes and let it stand for another 3 minutes but your medicine vial remains cloudy or has clumps, powder, or foreign particles. Call your pharmacy to get a new kit.

What should I do if the sterile water will not come out of the prefilled syringe?

Check that the vial adapter is attached to the vial securely. If not, hold the vial and press the vial adapter down firmly to make sure the vial adapter punctures the vial rubber stopper.

What should I do if I dropped my kit components?

Do not use if any items are damaged. If you are unsure, call your pharmacy to get a new kit.

Can I use my kit that has been left out of the refrigerator?

Store the injection kit in the refrigerator until ready to use it. If the unused injection kit has been out of the refrigerator up to 77°F (25°C) for more than 24 hours, please contact your pharmacy or healthcare provider.

Do I need to use mixed medicine right away?

We recommend you inject the medicine right away after mixing but no later than 4 hours after mixing. If it has been more than 4 hours, throw away unused mixed medicine. If you have questions, please contact your pharmacy or healthcare provider.

How can I get help preparing and giving my injection?

If you have questions about how to give WINREVAIR the correct way or need more information, you can call your pharmacy or healthcare provider.

Call your doctor for advice about side effects.

To report side effects or product quality complaints, please call Merck Sharp & Dohme LLC at 1-800-672-6372. You can also report side effects to FDA at 1-800-FDA-1088.

Manufactured by:
Merck Sharp & Dohme LLC
Rahway, NJ 07065, USA
U.S. License Number 0002

Copyright © 2024 Merck & Co., Inc., Rahway, NJ, USA, and its affiliates.
All rights reserved.

usifu1-mk7962-i-2403r000

This Instructions for Use has been approved by the U.S. Food and Drug Administration
Approved: March 2024

INSTRUCTIONS FOR USE

Important: Read this booklet first | Important
INSTRUCTIONS FOR USE | Mix
WINREVAIR™ (WIN-reh-vair) (sotatercept-csrk) for injection, for subcutaneous use How to use your WINREVAIR injection kit | Combine
For package containing 2 vials | Withdraw
For subcutaneous injection only (inject directly under the skin) | Inject

In this booklet:

Important information for patients or caregivers

Before you start

Get to know the parts of your kit

Important information you need to know before injecting WINREVAIR

Storing your injection kit

Get started

Mix powdered medicine into liquid form

Combine medicine from both vials

Withdraw your prescribed dose

Inject your medicine

How to throw away WINREVAIR

Frequently asked questions

Important information for patients or caregivers

Before you prepare and inject WINREVAIR, you must be:

- trained by a healthcare provider following this Instructions for Use booklet step-by-step, and
- capable of independent administration of WINREVAIR as determined by a healthcare provider

Before using WINREVAIR, make sure you are trained to do the following correctly:

1. Reconstitute (mix) the medicine
2. Combine medicine from both vials
3. Measure the correct amount of medicine according to your prescription
4. Select and prepare a proper injection site
5. Inject the medicine subcutaneously

Before you start:

Read this booklet
Read this Instructions for Use from start to finish before using WINREVAIR and each time you get a refill. There may be new information.

Start with your healthcare provider
Do not use WINREVAIR until your healthcare provider has shown you or your caregiver the right way to prepare and inject it. Your healthcare provider should show you how to inject WINREVAIR before you use it for the first time.

Questions?
If you have questions about how to give WINREVAIR the right way or need more information, call your pharmacy or healthcare provider.
For general product information visit www.WINREVAIR.com or call Merck Sharp & Dohme LLC at 1-800-672-6372.

How to use WINREVAIR

Before injecting WINREVAIR, make sure you read the full instructions in this booklet to get your prescribed dose.

Mix medicine in vial 1

Mix medicine in vial 2

Combine medicine mixture from vial 1 to vial 2

Withdraw your prescribed dose from vial 2

Then, inject your medicine

Proceed to the next pages for step-by-step directions.

Get to know the parts of your kit

Top Tray

Use to mix the medicine

2 Vials of WINREVAIR medicine powder

2 Prefilled syringes with sterile water for injection to mix medicine powder into liquid form

2 Vial adapters to connect the vial and syringe

Bottom Tray

Use to inject the medicine

Needle for injection

Empty dosing syringe to measure, withdraw, and inject your medicine

Important information you need to know before injecting WINREVAIR

- You must mix WINREVAIR before using it. Make sure the medicine powder in the vial is completely dissolved before you inject.
- Check your prescribed dose (amount in ‘mL’) each time you use WINREVAIR. Your prescribed dose may change. Your prescribed dose is on the prescription label on your kit.
- Use only the supplies that are in the kit to prepare your prescribed dose.
- Do not open the package or mix the medicine until you are ready to use it.
- Do not reuse any of the supplies. After your injection, throw away the used vials with any remaining WINREVAIR medicine, needle, caps, and syringes in a sharps container. See pages 38-39 for more information.

Storing your injection kit

Store WINREVAIR injection kit in the refrigerator at 36°F to 46°F (2°C to 8°C). Do not freeze.

Store in the original carton to protect from light.

Keep injection kit out of the reach of children and pets.

Get started

Before you can prepare and inject WINREVAIR, you must first be trained and determined to be capable of independent administration of WINREVAIR by a healthcare provider.

1 Check WINREVAIR injection kit and expiration date

Remove the WINREVAIR injection kit from the refrigerator.

Check the expiration date and look for any signs of damage on the kit or on the supplies.
If expired or damaged, do not use.
Call your pharmacy to get a new kit.

Check that you have the medicine that your healthcare provider prescribed.

2 Let your kit come to room temperature, gather supplies, and wash your hands

Wait 15 minutes to allow your kit to warm to room temperature.
Cold medicine is more painful to inject.

Along with your kit, gather these items and find a clean, flat surface where you will prepare and inject your dose.

Sharps disposal container

Gauze, cotton ball, or bandage

Wash your hands with soap and water.

Mix powdered medicine into liquid form

Start with the Top Tray

3 Remove medicine vial 1, prefilled syringe with sterile water for injection 1, alcohol wipes, and vial adapter 1 from the kit.

4a Check medicine vial

Check the vial label to confirm the medicine is not expired.

Inspect the medicine powder.
It should be white to off-white.

Do not use if expired, damaged, discolored, or you can see particles in it.

4b Remove plastic cap and clean vial

Flip off the plastic cap and clean the rubber stopper on top of the vial with an alcohol wipe.

Do not use if vial cap is missing.

Do not touch the cleaned rubber stopper.

Set vial aside on a clean, flat surface.

5a Align vial adapter to vial

Peel open the vial adapter package and remove vial adapter from its package. | Hold the blue neck of the vial adapter and align the vial adapter on top of the vial. Do not touch the inside of the vial adapter.

5b Attach vial adapter to vial

Hold the vial with one hand. Push down firmly so it snaps in place (you may feel some resistance).

5c Clean vial adapter

Clean the top of the vial adapter with an alcohol wipe.

6 Check prefilled syringe

Confirm the sterile water inside the prefilled syringe is clear and the product is not expired or leaking.
Do not use if you see any clumps, particles, discoloration, or product is expired. You might see air bubbles. This is okay.

7 Snap off prefilled syringe white cap

Snap off the prefilled syringe cap along the perforation.

8 Connect prefilled syringe to vial adapter

Pick up the vial with the vial adapter attached.
Align the prefilled syringe tip on the blue circle of the vial adapter.
Push then twist the prefilled syringe onto the vial adapter until you cannot turn further. While twisting, be sure to hold onto the vial adapter.

9 Transfer sterile water from prefilled syringe to vial

Slowly push the plunger all the way down to transfer all the sterile
water into the vial (the plunger will move up; this is normal).

Leave the prefilled syringe attached to the vial and set aside on a flat surface.

10 Prepare vial 2, prefilled syringe 2, and vial adapter 2

Stop and check to make sure you have both vial 1 and vial 2 prepared.

You need both vials prepared before you can continue to Step 11.

11 Swirl to mix medicine

Do not shake the vials. Hold 1 prefilled syringe in each hand and gently swirl both vials in a circular motion until the powder is fully dissolved. This may take up to 2 minutes. | When the medicine is mixed well, it should be clear. If not, repeat this step until it is clear. | For each vial, press the plunger down to make sure all the liquid is in the vial (the plunger will move up; this is normal).

12 Wait for large bubbles in the vials to go away

It is okay to have slight foam around edges of the vials | Set both vials aside for large bubbles to go away. This may take up to 3 minutes.

13 Prepare vials by removing extra air

Start with either vial. With the vial standing upright, gently pull the plunger upwards to the top of the barrel. Do not pull the plunger out of the syringe.

Note: Pulling extra air out of the vials will help to make sure you have the right dose.

14 Remove prefilled syringes from vials

Hold the vial adapters and unscrew both prefilled syringes from the vials. Throw away both prefilled syringes in the sharps container. | You should have 2 vials of medicine prepared and ready to be combined in the next steps.

Combine medicine from both vials

For the next steps, you will need:

1. Mixed vial 1 and vial 2
2. Items from the Bottom Tray (needle, dosing syringe for injection, and alcohol wipes).

15 Clean top of both vial adapters

With 2 alcohol wipes from the bottom tray, clean the top of the vial adapters. Use a new wipe for each vial adapter.

16 Remove empty dosing syringe from its package

Find the empty dosing syringe in the bottom tray and remove it from its package.

You will use this dosing syringe to combine medicine from both vials and measure out the medicine you need (based on your prescribed dose).

17 Pull air into the dosing syringe

You must do this to make sure pressure in the vial is even and you get an accurate dose.

Hold the dosing syringe upright and pull down the plunger to draw in 1.5 mL of air.

18 Connect dosing syringe to one of the vials

While holding the vial adapter, push then twist the dosing syringe onto the vial adapter until it stops.

19 Push air into vial, then flip upside down

Push the plunger all the way down to transfer all the air into the vial.
Then hold the plunger in place with your thumb and flip the vial upside down.

20 Withdraw all the medicine from 1st vial

With the vial and dosing syringe upside down, slowly pull the plunger back. Stop at 1.5 mL.
This will make sure all the medicine from the vial is in the dosing syringe.

21 Remove 1st vial from the dosing syringe

Hold the vial adapter and unscrew the filled dosing syringe from the vial.
Throw away the empty vial into the sharps container.

22 Connect the dosing syringe to the 2nd vial

While holding the vial adapter of the 2nd vial, push then twist the partially filled dosing syringe onto the vial adapter until it stops.

23 Push all the medicine into the 2nd vial, then flip vial upside down

Slowly push the plunger all the way down to transfer all of the medicine into the vial. This combines the medicine from both vials.
Hold the plunger in place with your thumb and flip the vial upside down.

Withdraw your prescribed dose

24 Pull plunger back to withdraw your prescribed dose

With the vial and dosing syringe upside down, slowly pull the plunger back.
Stop when you get to the amount in ‘mL’ that matches your prescribed dose.

25 Check for large bubbles and air pockets

Check to see if there are large air bubbles or an air pocket in the syringe. You will remove extra air in the next steps.

26 Remove air bubbles and air pockets from syringe

If you see large air bubbles or an air pocket, tap the side of the dosing syringe to move the air to the top.
Slowly push the plunger up to remove extra air.

27 Compare amount to prescribed dose

After removing all extra air, compare the amount in your syringe to your prescribed dose.
If you do not have your prescribed dose in your syringe, slowly pull the plunger back again to withdraw more medicine from the vial.
Repeat Steps 24 to 26 until you get your prescribed dose and no large bubbles or air pockets are visible.

28 Confirm your prescribed dose

Before you continue, check to make sure you have the prescribed dose in the dosing syringe.
If the amount does not match your prescribed dose, repeat Steps 24 to 27.

29 Remove the dosing syringe from the vial and set dosing syringe aside

Hold the plunger in place with one hand. With the other hand, hold the vial adapter and unscrew the filled dosing syringe from the vial.
Throw away the used vial into the sharps container.

Place the filled dosing syringe on a clean, flat surface.
Do not touch the dosing syringe tip or let it to touch any surfaces.

30 Attach injection needle to dosing syringe

Find the needle in the bottom tray and open its package. | With the needle still in the package, grip the base of the needle and twist on the dosing syringe until it stops. Remove the needle package. | Move the safety shield away from the needle and toward the syringe. Place the dosing syringe on a clean, flat surface. Do not uncap the needle.

31 Choose and clean your injection site

Select an injection site on your stomach (abdomen) or your upper thigh. If injecting on your stomach, avoid a 2-inch area around your belly button.
Choose a different site every time you inject.
Do not inject into skin that is damaged, sore, tender, bruised, or has red patches.
Do not inject through clothes.

Clean the injection site with a new alcohol wipe.
Do not touch the cleaned injection site again.

Now, you are ready to inject the medicine.

Inject your medicine

32 Inject your medicine

Pull the cap straight off the needle. Throw away the cap. Do not touch the plunger until ready to inject so you do not lose any medicine. | Gently pinch and hold a fold of skin where you will inject. Insert the needle with a dartlike motion at a 45° to 90° angle. | Push the plunger with slow, steady pressure all the way down until the dosing syringe is empty. Confirm all the medicine has been injected. You can let go of the skin fold now.

Keep your fingers away from the needle at all times.
While keeping the plunger pushed in, remove the needle from your skin at the same angle you inserted it. | To reapply the safety shield, push the shield against a flat surface until you hear a “click” and see that the needle is covered. | Throw away the dosing syringe and used items in a sharps container. Do not remove the needle from the dosing syringe.

How to throw away WINREVAIR

- Throw away any used vials (including any remaining WINREVAIR liquid), needle, vial and needle caps, and used syringes in an FDA-cleared sharps disposal container.
- Do not throw away the WINREVAIR vials, syringes, or needle in your household trash.
- Do not reuse any of the supplies.
  WINREVAIR is for one time use only.
- Important: Always keep the sharps disposal container out of reach of children and pets.

If you do not have an FDA-cleared sharps disposal container, you may use a household container that is:

- made of a heavy-duty plastic,
- can be closed with a tight-fitting, puncture-resistant lid, without sharp objects being able to come out,
- upright and stable during use,
- leak resistant, and
- properly labeled to warn of hazardous waste inside the container.

When your sharps disposal container is almost full, you will need to follow your community guidelines for the right way to throw away your sharps container. There may be state or local laws about how you should throw away used needles, dosing syringes, and prefilled syringes.

For more information about safe sharps disposal, and for specific information about sharps disposal in the state that you live in, go to the FDA’s website at: http://www.fda.gov/safesharpsdisposal.
Do not recycle your used sharps container.

Frequently asked questions

What should I do if I am bleeding at the injection site?

Place a cotton ball or bandage on your skin right away and apply a small amount of pressure. If the bleeding does not stop, call your healthcare provider right away.

Where can I find my prescribed dose?

Your prescribed dose in ‘mL’ is on your prescription label on your kit. Contact your healthcare provider if you cannot find your prescribed dose.

What should I do if I accidentally get some medicine on my skin or my work surface?

Wash the area thoroughly with soap and water right away.

What should I do if I am not sure I administered my prescribed dose correctly?

Call your pharmacy or healthcare provider.

What should I do if the plunger of my dosing syringe moves automatically when I try to withdraw medicine from the vial?

Do not worry if your plunger moves slightly on its own when you are filling your dosing syringe with medicine.

With one hand, hold the plunger in place to stop the plunger from moving. With the other hand, unscrew the vial from the dosing syringe.

After unscrewed, it is safe to let go of the plunger.

You can avoid this automatic plunger movement by pushing air into the vial before filling your dosing syringe with medicine. Refer to Steps 17 to 28 for detailed instructions.

What should I do if my kit parts are damaged or are discolored, cloudy, or have particles?

Do not use your kit. Call your pharmacy to get a new kit.

What should I do if my medicine does not turn clear after mixing and swirling?

Do not use the medicine if you have swirled the medicine vial for about 2 minutes and let it stand for another 3 minutes but your medicine vial remains cloudy or has clumps, powder, or foreign particles. Call your pharmacy to get a new kit.

What should I do if the sterile water will not come out of the prefilled syringe?

Check that the vial adapter is attached to the vial securely. If not, hold the vial and press the vial adapter down firmly to make sure the vial adapter punctures the vial rubber stopper.

What should I do if I dropped my kit components?

Do not use if any items are damaged. If you are unsure, call your pharmacy to get a new kit.

Can I use my kit that has been left out of the refrigerator?

Store the injection kit in the refrigerator until ready to use it. If the unused injection kit has been out of the refrigerator up to 77°F (25°C) for more than 24 hours, please contact your pharmacy or healthcare provider.

Do I need to use mixed medicine right away?

We recommend you inject the medicine right away after mixing but no later than 4 hours after mixing. If it has been more than 4 hours, throw away unused mixed medicine. If you have questions, please contact your pharmacy or healthcare provider.

How can I get help preparing and giving my injection?

If you have questions about how to give WINREVAIR the correct way or need more information, you can call your pharmacy or healthcare provider.

Call your doctor for advice about side effects.

To report side effects or product quality complaints, please call Merck Sharp & Dohme LLC at 1-800-672-6372. You can also report side effects to FDA at 1-800-FDA-1088.

Manufactured by:
Merck Sharp & Dohme LLC
Rahway, NJ 07065, USA
U.S. License Number 0002

Copyright © 2024 Merck & Co., Inc., Rahway, NJ, USA, and its affiliates.
All rights reserved.

usifu2-mk7962-i-2403r000

This Instructions for Use has been approved by the U.S. Food and Drug Administration

Approved: March 2024

PRINCIPAL DISPLAY PANEL - 45 mg Vial Kit Carton

NDC 0006-5090-01

WINREVAIR™
(sotatercept-csrk) for injection

45 mg/vial

Package
contains
1 Vial

Dose
based on
patient
weight

For Subcutaneous Use Only
Must be reconstituted with diluent provided
prior to administration

1 Single-Dose Vial
Discard unused portion

Rx only

PRINCIPAL DISPLAY PANEL - 60 mg Vial Kit Carton

NDC 0006-5091-01

WINREVAIR™
(sotatercept-csrk) for injection

60 mg/vial

Package
contains
1 Vial

Dose
based on
patient
weight

For Subcutaneous Use Only
Must be reconstituted with diluent provided
prior to administration

1 Single-Dose Vial
Discard unused portion

Rx only

PRINCIPAL DISPLAY PANEL - 45 mg 2 Vials Kit Carton

NDC 0006-5087-01

WINREVAIR™
(sotatercept-csrk) for injection

45 mg/vial

Package
contains
2 Vials

Dose
based on
patient
weight

For Subcutaneous Use Only
Must be reconstituted with diluent provided
prior to administration

2 Single-Dose Vials
Discard unused portion

Rx only

PRINCIPAL DISPLAY PANEL - 60 mg 2 Vials Kit Carton

NDC 0006-5088-01

WINREVAIR™
(sotatercept-csrk) for injection

60 mg/vial

Package
contains
2 Vials

Dose
based on
patient
weight

For Subcutaneous Use Only
Must be reconstituted with diluent provided
prior to administration

2 Single-Dose Vials
Discard unused portion

Rx only